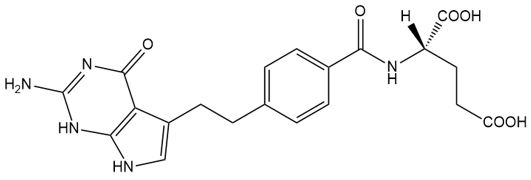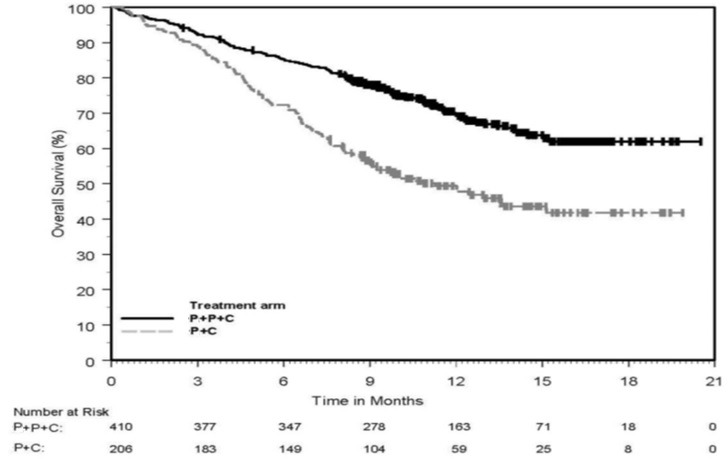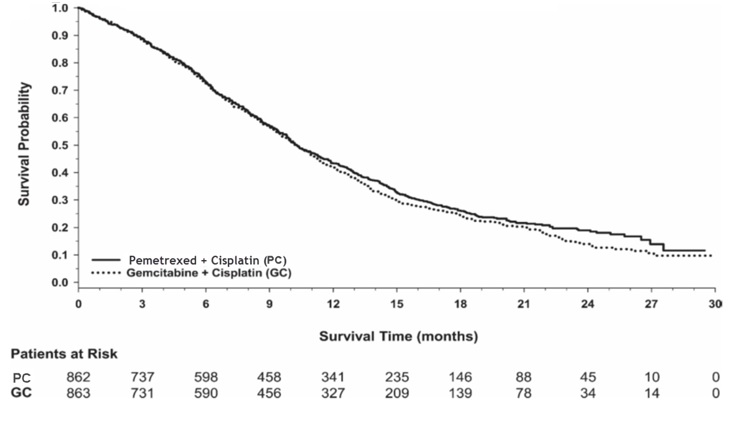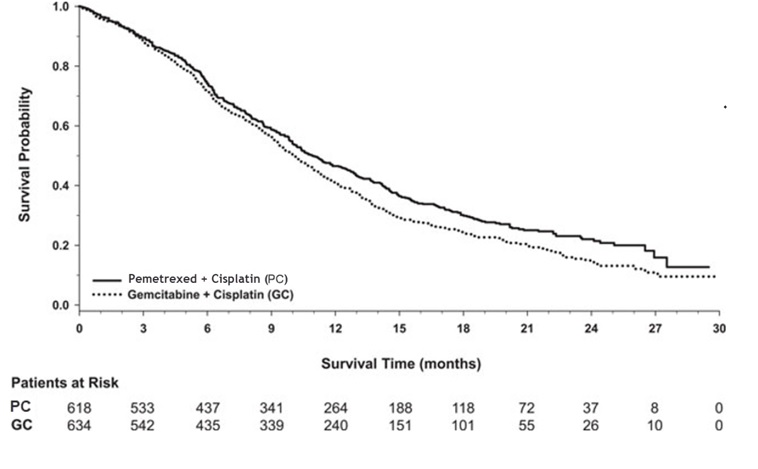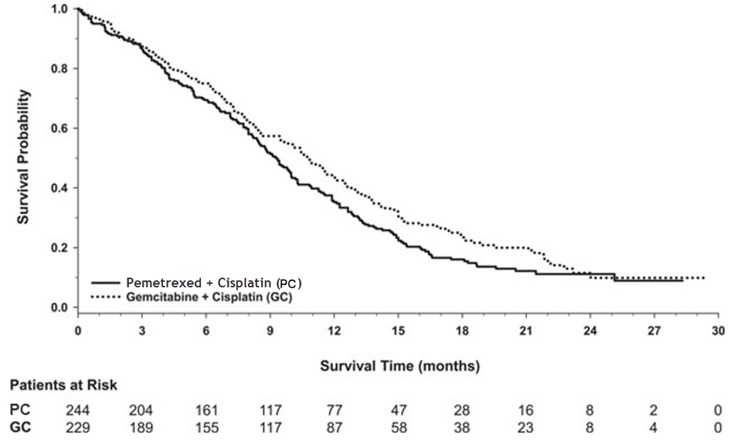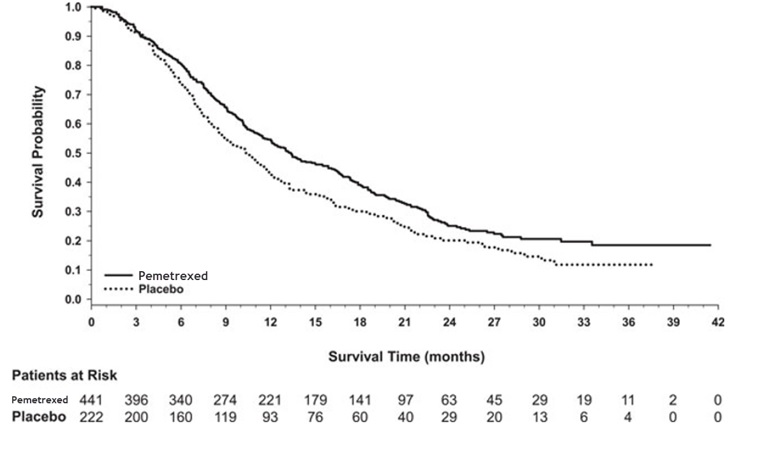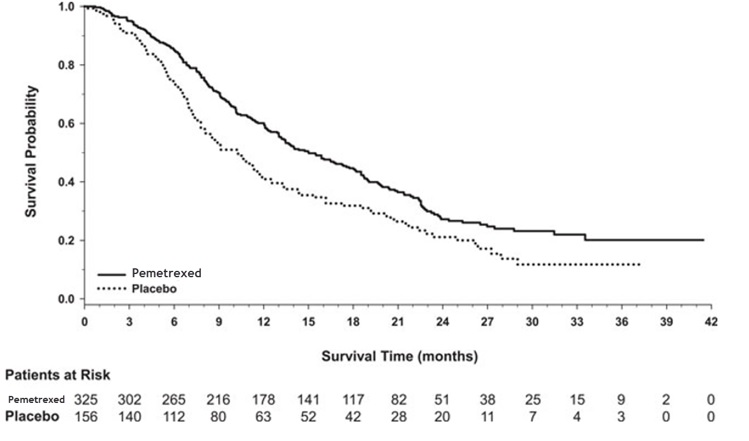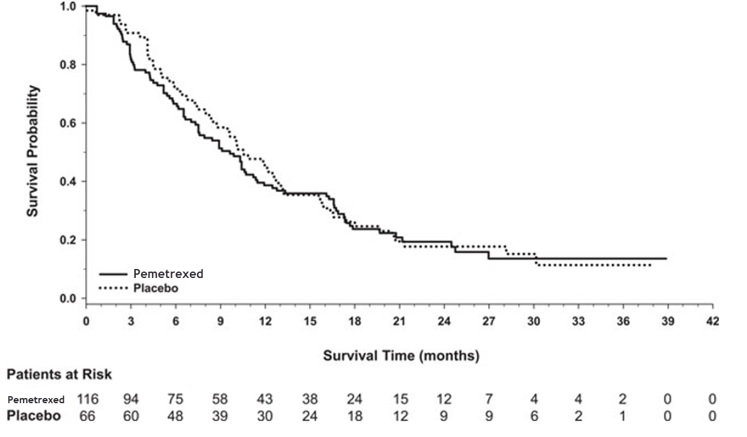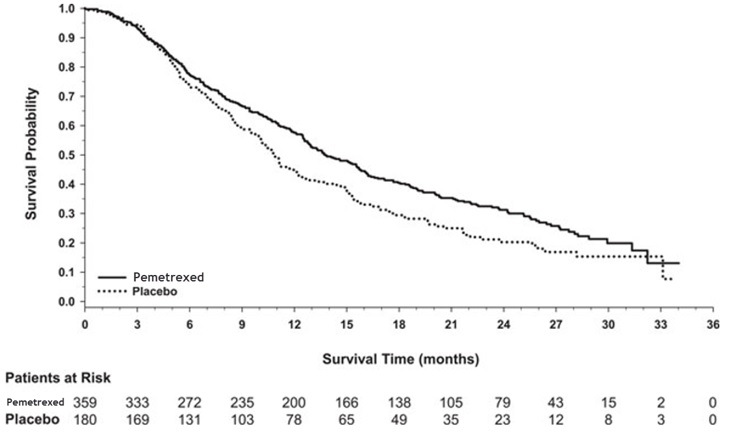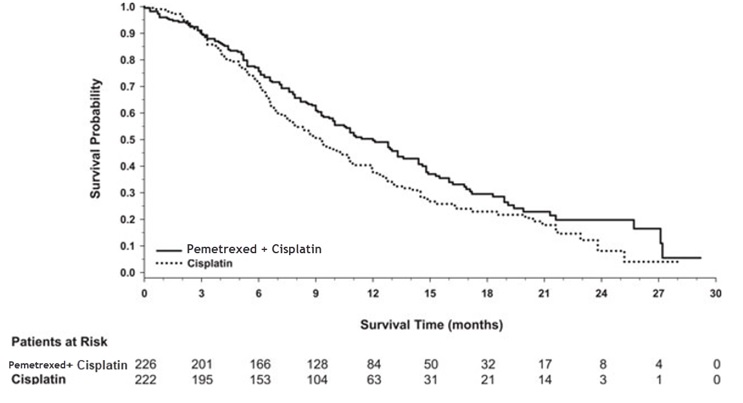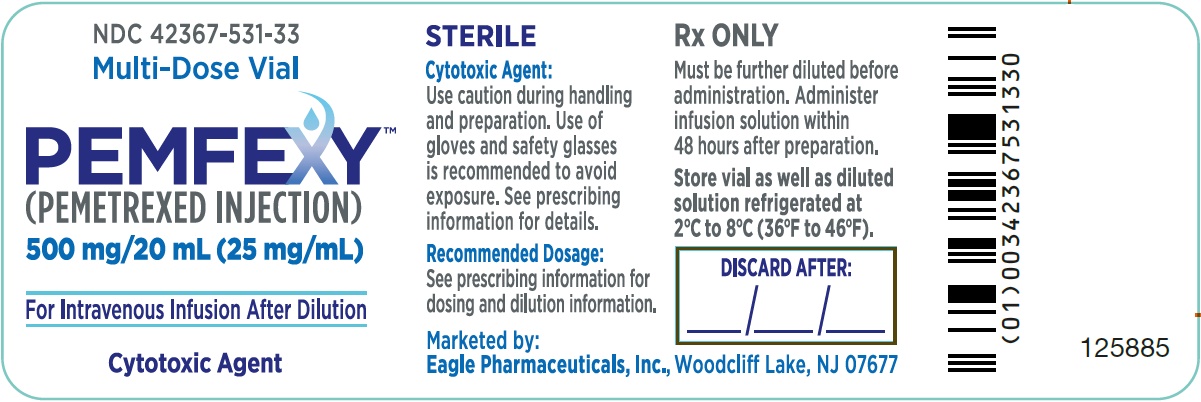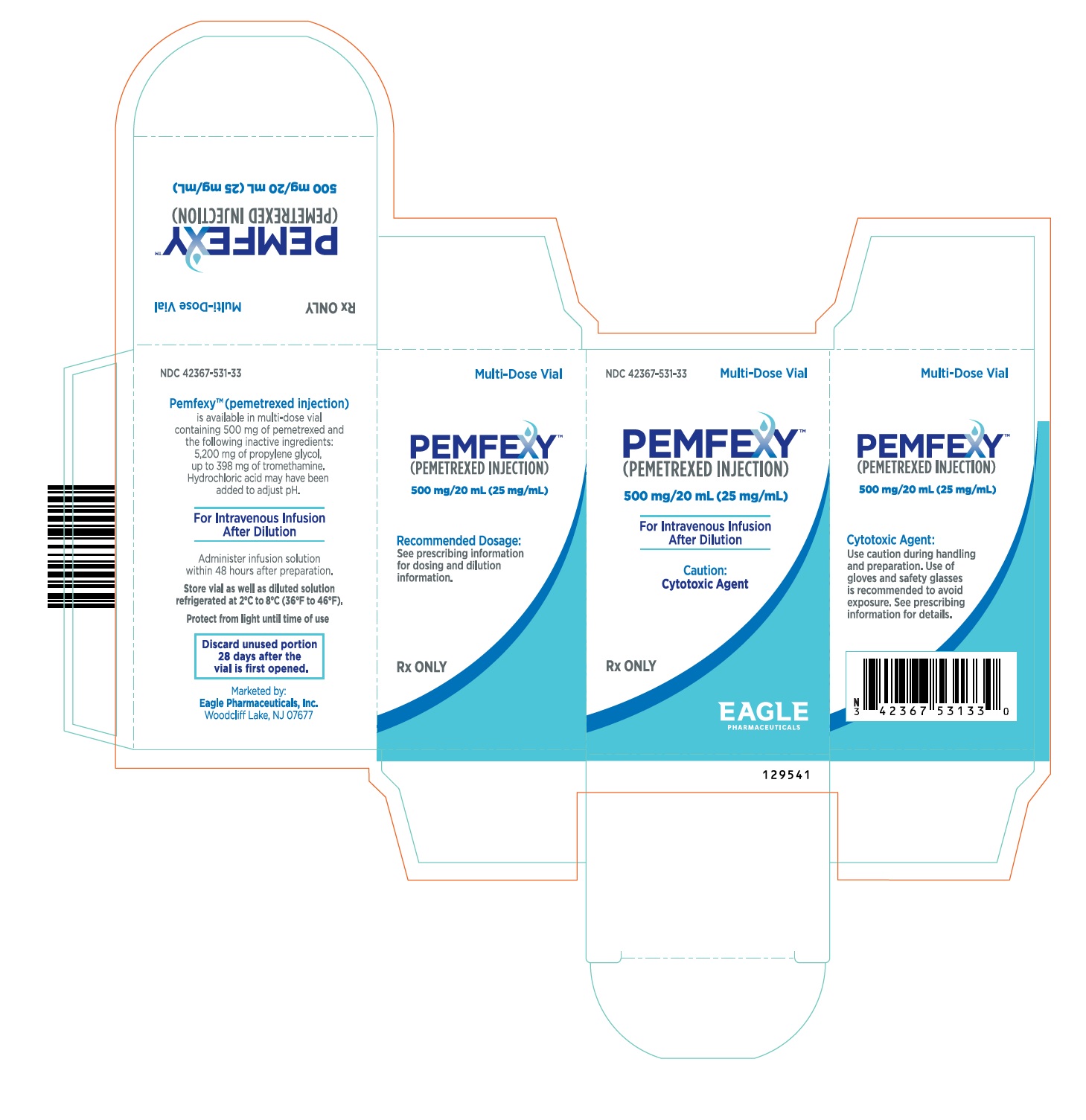 DRUG LABEL: Pemfexy
NDC: 42367-531 | Form: INJECTION
Manufacturer: Eagle Pharmaceuticals, Inc.
Category: prescription | Type: HUMAN PRESCRIPTION DRUG LABEL
Date: 20260220

ACTIVE INGREDIENTS: PEMETREXED MONOHYDRATE 25 mg/1 mL
INACTIVE INGREDIENTS: PROPYLENE GLYCOL 260 mg/1 mL; TROMETHAMINE; HYDROCHLORIC ACID; NITROGEN

HIGHLIGHTS OF PRESCRIBING INFORMATION

These highlights do not include all the information needed to use PEMFEXY safely and effectively. See full prescribing information for PEMFEXY.
PEMFEXY™ (pemetrexed injection), for intravenous use
Initial U.S. Approval: 2004

1 INDICATIONS AND USAGE

PEMFEXY™ is a folate analog metabolic inhibitor indicated for:

- in combination with pembrolizumab and platinum chemotherapy, for the initial treatment of patients with metastatic non-squamous NSCLC, with no EGFR or ALK genomic tumor aberrations. (1.1)
- in combination with cisplatin for the initial treatment of patients with locally advanced or metastatic non-squamous, non-small cell lung cancer (NSCLC). (1.1)
- as a single agent for the maintenance treatment of patients with locally advanced or metastatic non-squamous NSCLC whose disease has not progressed after four cycles of platinum-based first-line chemotherapy. (1.1)
- as a single agent for the treatment of patients with recurrent, metastatic non-squamous NSCLC after prior chemotherapy. (1.1)
  Limitations of Use: PEMFEXY is not indicated for the treatment of patients with squamous cell non-small cell lung cancer. (1.1)
- in combination with cisplatin for the initial treatment, of patients with malignant pleural mesothelioma whose disease is unresectable or who are otherwise not candidates for curative surgery. (1.2)

2 DOSAGE AND ADMINISTRATION

- The recommended dose of PEMFEXY administered with pembrolizumab and platinum chemotherapy in patients with a creatinine clearance (calculated by Cockcroft-Gault equation) of 45 mL/min or greater is 500 mg/m^2 as an intravenous infusion over 10 minutes, administered after pembrolizumab and prior to platinum chemotherapy, on Day 1 of each 21-day cycle. (2.1)
- The recommended dosage of PEMFEXY, administered as a single agent or with cisplatin, in patients with creatinine clearance of 45 mL/minute or greater, is 500 mg/m^2 as an intravenous infusion over 10 minutes on Day 1 of each 21-day cycle. (2.1, 2.2, 2.3)
- Initiate folic acid 400 mcg to 1000 mcg orally once daily beginning 7 days prior to the first dose of PEMFEXY and continue until 21 days after the last dose. (2.4)
- Administer vitamin B12 1 mg intramuscularly 1 week prior to the first dose of PEMFEXY and every 3 cycles thereafter. (2.4)
- Administer dexamethasone 4 mg orally twice daily the day before, the day of, and the day after PEMFEXY administration. (2.4)

3 DOSAGE FORMS AND STRENGTHS

- Injection: 500 mg/20 mL (25 mg/mL) in a multi-dose vial (3)

4 CONTRAINDICATIONS

- History of severe hypersensitivity reaction to pemetrexed. (4)

5 WARNINGS AND PRECAUTIONS

- Myelosuppression: Can cause severe bone marrow suppression resulting in cytopenia and an increased risk of infection. Do not administer PEMFEXY when the absolute neutrophil count is less than 1500 cells/mm^3 and platelets are less than 100,000 cells/mm^3. Initiate supplementation with oral folic acid and intramuscular vitamin B12 to reduce the severity of hematologic and gastrointestinal toxicity of PEMFEXY. (2.4, 5.1)
- Renal Failure: Can cause severe, and sometimes fatal, renal failure. Do not administer when creatinine clearance is less than 45 mL/min (2.3, 5.2)
- Bullous and Exfoliative Skin Toxicity: Permanently discontinue for severe and life-threatening bullous, blistering or exfoliating skin toxicity. (5.3)
- Interstitial Pneumonitis: Withhold for acute onset of new or progressive unexplained pulmonary symptoms. Permanently discontinue if pneumonitis is confirmed. (5.4)
- Radiation Recall: Can occur in patients who received radiation weeks to years previously; permanently discontinue for signs of radiation recall. (5.5)
- Embryo-Fetal Toxicity: Can cause fetal harm. Advise patients of the potential risk to a fetus and to use effective contraception. (5.7, 8.1, 8.3)

6 ADVERSE REACTIONS

- The most common adverse reactions (incidence ≥ 20%) of pemetrexed, when administered as a single agent are fatigue, nausea, and anorexia. (6.1)
- The most common adverse reactions (incidence ≥ 20%) of pemetrexed when administered with cisplatin are vomiting, neutropenia, anemia, stomatitis/pharyngitis, thrombocytopenia, and constipation. (6.1)
- The most common adverse reactions (incidence ≥20%) of pemetrexed when administered in combination with pembrolizumab and platinum chemotherapy are fatigue/asthenia, nausea, constipation, diarrhea, decreased appetite, rash, vomiting, cough, dyspnea, and pyrexia. (6.1)

To report SUSPECTED ADVERSE REACTIONS, contact Eagle Pharmaceuticals, Inc. at 1-855-318-2170 or FDA at 1-800-FDA-1088 or www.fda.gov/medwatch.

7 DRUG INTERACTIONS

Ibuprofen: Modify the ibuprofen dosage as recommended for patients with a creatinine clearance between 45 mL/min and 79 mL/min. (2.5, 5.6, 7)

8 USE IN SPECIFIC POPULATIONS

Lactation: Advise not to breastfeed. (8.2)

FULL PRESCRIBING INFORMATION

1 INDICATIONS AND USAGE

1.1 Non-squamous Non-Small Cell Lung Cancer

PEMFEXY™ is indicated:

- in combination with pembrolizumab and platinum chemotherapy, for the initial treatment of patients with metastatic non-squamous non-small cell lung cancer (NSCLC), with no EGFR or ALK genomic tumor aberrations.
- in combination with cisplatin for the initial treatment of patients with locally advanced or metastatic, non-squamous NSCLC.
- as a single agent for the maintenance treatment of patients with locally advanced or metastatic non-squamous NSCLC whose disease has not progressed after four cycles of platinum-based first-line chemotherapy.
- as a single agent for the treatment of patients with recurrent, metastatic non-squamous NSCLC after prior chemotherapy.

Limitations of Use: PEMFEXY is not indicated for the treatment of patients with squamous cell NSCLC [see Clinical Studies 14.1].

1.2 Mesothelioma

PEMFEXY is indicated in combination with cisplatin for the initial treatment of patients with malignant pleural mesothelioma whose disease is unresectable or who are otherwise not candidates for curative surgery.

2 DOSAGE AND ADMINISTRATION

2.1 Recommended Dosage for Non-squamous Non-Small Cell Lung Cancer

- The recommended dose of PEMFEXY, when administered with pembrolizumab and platinum chemotherapy for the initial treatment of metastatic non-squamous NSCLC in patients with a creatinine clearance (calculated by Cockcroft-Gault equation) of 45 mL/min or greater is 500 mg/m^2 as an intravenous infusion over 10 minutes administered after pembrolizumab and prior to carboplatin or cisplatin on Day 1 of each 21-day cycle for 4 cycles. Following completion of platinum-based therapy, treatment with PEMFEXY with or without pembrolizumab is administered until disease progression or unacceptable toxicity. Please refer to the full prescribing information for pembrolizumab and for carboplatin or cisplatin.
- The recommended dosage of PEMFEXY, when administered with cisplatin for initial treatment of locally advanced or metastatic non-squamous NSCLC in patients with a creatinine clearance (calculated by Cockcroft-Gault equation) of 45 mL/min or greater, is 500 mg/m^2 as an intravenous infusion over 10 minutes administered prior to cisplatin on Day 1 of each 21-day cycle for up to six cycles in the absence of disease progression or unacceptable toxicity.
- The recommended dosage of PEMFEXY for maintenance treatment of non-squamous NSCLC in patients with a creatinine clearance (calculated by Cockcroft-Gault equation) of 45 mL/min or greater is 500 mg/m^2 as an intravenous infusion over 10 minutes on Day 1 of each 21-day cycle until disease progression or unacceptable toxicity after four cycles of platinum-based first-line chemotherapy.
- The recommended dosage of PEMFEXY for treatment of recurrent non-squamous NSCLC in patients with a creatinine clearance (calculated by Cockcroft-Gault equation) of 45 mL/min or greater is 500 mg/m^2 as an intravenous infusion over 10 minutes on Day 1 of each 21-day cycle until disease progression or unacceptable toxicity.

2.2 Recommended Dosage for Mesothelioma

The recommended dosage of PEMFEXY, when administered with cisplatin, in patients with a creatinine clearance (calculated by Cockcroft-Gault equation) of 45 mL/min or greater is 500 mg/m^2 as an intravenous infusion over 10 minutes on Day 1 of each 21-day cycle until disease progression or unacceptable toxicity.

2.3 Renal Impairment

PEMFEXY dosing recommendations are provided for patients with a creatinine clearance (calculated by Cockcroft-Gault equation) of 45 mL/min or greater [see Dosage and Administration (2.1, 2.2)]. There is no recommended dose for patients whose creatinine clearance is less than 45 mL/min [see Use in Specific Populations (8.6)].

2.4 Premedication and Concomitant Medications to Mitigate Toxicity

Vitamin Supplementation
Initiate folic acid 400 mcg to 1000 mcg orally once daily, beginning 7 days before the first dose of PEMFEXY and continuing until 21 days after the last dose [see Warnings and Precautions (5.1)].

Administer vitamin B12 1 mg intramuscularly 1 week prior to the first dose of PEMFEXY and every 3 cycles thereafter. Subsequent vitamin B12 injections may be given the same day as treatment with PEMFEXY [see Warnings and Precautions (5.1)]. Do not substitute oral vitamin B12 for intramuscular vitamin B12.

Corticosteroids
Administer dexamethasone 4 mg orally twice daily for three consecutive days, beginning the day before each PEMFEXY administration.

2.5 Dosage Modification of Ibuprofen in Patients with Mild to Moderate Renal Impairment Receiving PEMFEXY

In patients with creatinine clearances between 45 mL/min and 79 mL/min, modify administration of ibuprofen as follows [see Warnings and Precautions (5.6), Drug Interactions (7) and Clinical Pharmacology (12.3)].

- Avoid administration of ibuprofen for 2 days before, the day of, and 2 days following administration of PEMFEXY.
- Monitor patients more frequently for myelosuppression, renal, and gastrointestinal toxicity, if concomitant administration of ibuprofen cannot be avoided.

2.6 Dosage Modifications for Adverse Reactions

Obtain complete blood count on Days 1, 8, and 15 of each cycle. Assess creatinine clearance prior to each cycle. Do not administer PEMFEXY if the creatinine clearance is less than 45 mL/min.

Delay initiation of the next cycle of PEMFEXY until:

- Recovery of non-hematologic toxicity to Grade 0-2,
- Absolute neutrophil count (ANC) is 1500 cells/mm^3 or higher, and
- Platelet count is 100,000 cells/mm^3 or higher.

Upon recovery, modify the dosage of PEMFEXY in the next cycle as specified in Table 1.

For dosing modifications for cisplatin, carboplatin, or pembrolizumab, refer to their prescribing information.

Table 1: Recommended Dosage Modifications for Adverse Reactionsa
Toxicity in Most Recent Treatment Cycle | PEMFEXY Dosage Modifications for Next Cycle
Myelosuppressive toxicity [see Warnings and Precautions (5.1)]
ANC less than 500/mm^3 and platelets greater than or equal to 50,000/mm^3 OR Platelet count less than 50,000/mm^3 without bleeding. | 75% of previous dose
Platelet count less than 50,000/mm^3 with bleeding | 50% of previous dose
Recurrent Grade 3 or 4 myelosuppression after 2 dose reductions | Permanently discontinue.
Non-hematologic toxicity
Any Grade 3 or 4 toxicities EXCEPT mucositis or neurologic toxicity OR Diarrhea requiring hospitalization | 75% of previous dose
Grade 3 or 4 mucositis | 50% of previous dose
Renal toxicity [see Warnings and Precautions (5.2)] | Withhold until creatinine clearance is 45 mL/min or greater.
Grade 3 or 4 neurologic toxicity | Permanently discontinue.
Recurrent Grade 3 or 4 non-hematologic toxicity after 2 dose reductions | Permanently discontinue.
Severe and life-threatening skin toxicity [see Warnings and Precautions (5.3)] | Permanently discontinue.
Interstitial pneumonitis [see Warnings and Precautions (5.4)] | Permanently discontinue.
a National Cancer Institute Common Toxicity Criteria for Adverse Events version 2 (NCI CTCAE v2)

2.7 Preparation and Administration

PEMFEXY is a hazardous drug. Follow applicable special handling and disposal procedures.^1

Calculate the dose of PEMFEXY and determine the number of vials needed. Withdraw the calculated dose of PEMFEXY from the vial(s). Store unused portion in vial refrigerated at 2°C to 8°C (36°F to 46°F) for up to 28 days. Each vial contains 500 mg pemetrexed per 20 mL (25 mg/mL). The vial contains an excess of pemetrexed to facilitate delivery of labeled amount.

- Dilute PEMFEXY with 5% Dextrose in Water, USP or Normal Saline to achieve a total volume of 100 mL for intravenous infusion. Do not use other diluents, such as Lactated Ringer’s Injection, USP or Ringer’s Injection, USP.
- Visually inspect for particulate matter and discoloration prior to administration, whenever solution and container permit. Discard if particulate matter or discoloration is observed.
- Administer PEMFEXY as an intravenous infusion over 10 minutes.
- Store diluted PEMFEXY refrigerated at 2°C to 8°C (36 °F to 46°F) for no more than 48 hours. PEMFEXY diluted with 5% Dextrose in Water, USP can also be stored at ambient room temperature and room light for no more than 48 hours. When prepared as directed, infusion solutions of PEMFEXY contain no antimicrobial preservatives. Discard after 48 hours.

PEMFEXY is compatible with polyolefin infusion bags with polyvinyl chloride (PVC) ports.

3 DOSAGE FORMS AND STRENGTHS

Injection: 500 mg pemetrexed per 20 mL (25 mg/mL) as a clear, colorless to yellow or green-yellow solution in a multi-dose vial.

4 CONTRAINDICATIONS

PEMFEXY is contraindicated in patients with a history of severe hypersensitivity reaction to pemetrexed [see Adverse Reactions (6.1)].

5 WARNINGS AND PRECAUTIONS

5.1 Myelosuppression and Increased Risk of Myelosuppression without Vitamin Supplementation

Pemetrexed can cause severe myelosuppression resulting in a requirement for transfusions and which may lead to neutropenic infection. The risk of myelosuppression is increased in patients who do not receive vitamin supplementation. In Study JMCH, incidences of Grade 3-4 neutropenia (38% versus 23%), thrombocytopenia (9% versus 5%), febrile neutropenia (9% versus 0.6%), and neutropenic infection (6% versus 0) were higher in patients who received pemetrexed plus cisplatin without vitamin supplementation as compared to patients who were fully supplemented with folic acid and vitamin B12 prior to and throughout pemetrexed plus cisplatin treatment.

Initiate supplementation with oral folic acid and intramuscular vitamin B12 prior to the first dose of PEMFEXY; continue vitamin supplementation during treatment and for 21 days after the last dose of PEMFEXY to reduce the severity of hematologic and gastrointestinal toxicity of pemetrexed [see Dosage and Administration (2.4)].

Obtain a complete blood count at the beginning of each cycle. Do not administer PEMFEXY until the ANC is at least 1500 cells/mm^3 and platelet count is at least 100,000 cells/mm^3. Permanently reduce PEMFEXY in patients with an ANC of less than 500 cells/mm^3 or platelet count of less than 50,000 cells/mm^3 in previous cycles [see Dosage and Administration (2.6)].

In Studies JMDB and JMCH, among patients who received vitamin supplementation, incidence of Grade 3-4 neutropenia was 15% and 23%, the incidence of Grade 3-4 anemia was 6% and 4%, and incidence of Grade 3-4 thrombocytopenia was 4% and 5%, respectively. In Study JMCH, 18% of patients in the pemetrexed arm required red blood cell transfusions compared to 7% of patients in the cisplatin arm [see Adverse Reactions (6.1)]. In Studies JMEN, PARAMOUNT and JMEI, where all patients received vitamin supplementation, incidence of Grade 3-4 neutropenia ranged from 3% to 5%, and incidence of Grade 3-4 anemia ranged from 3% to 5%.

5.2 Renal Failure

Pemetrexed can cause severe, and sometimes fatal, renal toxicity. The incidences of renal failure in clinical studies in which patients received pemetrexed with cisplatin were: 2.1% in Study JMDB and 2.2% in Study JMCH. The incidence of renal failure in clinical studies in which patients received pemetrexed as a single agent ranged from 0.4% to 0.6% (Studies JMEN, PARAMOUNT and JMEI [see Adverse Reactions (6.1)].

Determine creatinine clearance before each dose and periodically monitor renal function during treatment with PEMFEXY. Withhold PEMFEXY in patients with a creatinine clearance of less than 45 mL/minute [see Dosage and Administration (2.3)].

5.3 Bullous and Exfoliative Skin Toxicity

Serious and sometimes fatal, bullous, blistering and exfoliative skin toxicity, including cases suggestive of Stevens-Johnson syndrome/toxic epidermal necrolysis can occur with pemetrexed. Permanently discontinue PEMFEXY for severe and life-threatening bullous, blistering or exfoliating skin toxicity.

5.4 Interstitial Pneumonitis

Serious interstitial pneumonitis, including fatal cases, can occur with pemetrexed. Withhold PEMFEXY for acute onset of new or progressive unexplained pulmonary symptoms such as dyspnea, cough, or fever pending diagnostic evaluation. If pneumonitis is confirmed, permanently discontinue PEMFEXY.

5.5 Radiation Recall

Radiation recall can occur with pemetrexed in patients who have received radiation weeks to years previously. Monitor patients for inflammation or blistering in areas of previous radiation treatment. Permanently discontinue PEMFEXY for signs of radiation recall.

5.6 Increased Risk of Toxicity with Ibuprofen in Patients with Renal Impairment

Exposure to pemetrexed is increased in patients with mild to moderate renal impairment who take concomitant ibuprofen, increasing the risks of adverse reactions of pemetrexed. In patients with creatinine clearances between 45 mL/min and 79 mL/min, avoid administration of ibuprofen for 2 days before, the day of, and 2 days following administration of PEMFEXY. If concomitant ibuprofen use cannot be avoided, monitor patients more frequently for pemetrexed adverse reactions, including myelosuppression, renal, and gastrointestinal toxicity [see Dosage and Administration (2.5), Drug Interactions (7), and Clinical Pharmacology (12.3)].

5.7 Embryo-Fetal Toxicity

Based on findings from animal studies and its mechanism of action, pemetrexed can cause fetal harm when administered to a pregnant woman. In animal reproduction studies, intravenous administration of pemetrexed to pregnant mice during the period of organogenesis was teratogenic, resulting in developmental delays and increased malformations at doses lower than the recommended human dose of 500 mg/m2. Advise pregnant women of the potential risk to a fetus. Advise females of reproductive potential to use effective contraception during treatment with PEMFEXY and for 6 months after the last dose. Advise males with female partners of reproductive potential to use effective contraception during treatment with PEMFEXY and for 3 months after the last dose [see Use in Specific Populations (8.1, 8.3)].

6 ADVERSE REACTIONS

The following clinically significant adverse reactions are described elsewhere in the labeling:

- Myelosuppression [see Warnings and Precautions (5.1)]
- Renal failure [see Warnings and Precautions (5.2)]
- Bullous and exfoliative skin toxicity [see Warnings and Precautions (5.3)]
- Interstitial pneumonitis [see Warnings and Precautions (5.4)]
- Radiation recall [see Warnings and Precautions (5.5)]

6.1 Clinical Trials Experience

Because clinical trials are conducted under widely varying conditions, adverse reactions rates observed in clinical trials of drugs cannot be directly compared to rates in the clinical trials of another drug and may not reflect the rates observed in practice.

In clinical trials, the most common adverse reactions (incidence ≥ 20%) of pemetrexed, when administered as a single-agent, are fatigue, nausea and anorexia. The most common adverse reactions (incidence ≥ 20%) of pemetrexed, when administered with cisplatin, are vomiting, neutropenia, anemia, stomatitis/pharyngitis, thrombocytopenia and constipation. The most common adverse reactions (incidence ≥20%) of pemetrexed, when administered in combination with pembrolizumab and platinum chemotherapy, are fatigue/asthenia, nausea, constipation, diarrhea, decreased appetite, rash, vomiting, cough, dyspnea, and pyrexia.

Non-Squamous Non-Small Cell Lung Cancer (NSCLC)
First-line Treatment of Metastatic Non-squamous NSCLC with Pembrolizumab and Platinum Chemotherapy
The safety of pemetrexed, in combination with pembrolizumab and investigator’s choice of platinum (either carboplatin or cisplatin), was investigated in Study KEYNOTE-189, a multicenter, double-blind, randomized (2:1), active-controlled trial in patients with previously untreated, metastatic non-squamous NSCLC with no EGFR or ALK genomic tumor aberrations. A total of 607 patients received pemetrexed, pembrolizumab, and platinum every 3 weeks for 4 cycles followed by pemetrexed and pembrolizumab (n=405), or placebo, pemetrexed, and platinum every 3 weeks for 4 cycles followed by placebo and pemetrexed (n=202). Patients with autoimmune disease that required systemic therapy within 2 years of treatment; a medical condition that required immunosuppression; or who had received more than 30 Gy of thoracic radiation within the prior 26 weeks were ineligible [see Clinical Studies (14.1)].

The median duration of exposure to pemetrexed was 7.2 months (range: 1 day to 1.7 years). Seventy-two percent of patients received carboplatin. The study population characteristics were: median age of 64 years (range: 34 to 84), 49% age 65 years or older, 59% male, 94% White and 3% Asian, and 18% with history of brain metastases at baseline.

Pemetrexed was discontinued for adverse reactions in 23% of patients in the pemetrexed, pembrolizumab, and platinum arm. The most common adverse reactions resulting in discontinuation of pemetrexed in this arm were acute kidney injury (3%) and pneumonitis (2%). Adverse reactions leading to interruption of pemetrexed occurred in 49% of patients in the pemetrexed, pembrolizumab, and platinum arm. The most common adverse reactions or laboratory abnormalities leading to interruption of pemetrexed in this arm (≥2%) were neutropenia (12%), anemia (7%), asthenia (4%), pneumonia (4%), thrombocytopenia (4%), increased blood creatinine (3%), diarrhea (3%), and fatigue (3%).

Table 2 summarizes the adverse reactions that occurred in ≥20% of patients treated with pemetrexed, pembrolizumab, and platinum.

Table 2: Adverse Reactions Occurring in ≥20% of Patients in KEYNOTE-189
Adverse Reaction | Pemetrexed Pembrolizumab Platinum Chemotherapy n=405 |  | Placebo Pemetrexed Platinum Chemotherapy n=202
Adverse Reaction | All Gradesa(%) | Grade 3-4 (%) | All Grades (%) | Grade 3-4 (%)
Gastrointestinal Disorders
Nausea | 56 | 3.5 | 52 | 3.5
Constipation | 35 | 1.0 | 32 | 0.5
Diarrhea | 31 | 5 | 21 | 3.0
Vomiting | 24 | 3.7 | 23 | 3.0
General Disorders and Administration Site Conditions
Fatigueb | 56 | 12 | 58 | 6
Pyrexia | 20 | 0.2 | 15 | 0
Metabolism and Nutrition Disorders
Decreased appetite | 28 | 1.5 | 30 | 0.5
Skin and Subcutaneous Tissue Disorders
Rashc | 25 | 2.0 | 17 | 2.5
Respiratory, Thoracic and Mediastinal Disorders
Cough | 21 | 0 | 28 | 0
Dyspnea | 21 | 3.7 | 26 | 5
a Graded per NCI CTCAE version 4.03.
b Includes asthenia and fatigue.
c Includes genital rash, rash, rash generalized, rash macular, rash maculo-papular, rash papular, rash pruritic, and rash pustular.

Table 3 summarizes the laboratory abnormalities that worsened from baseline in at least 20% of patients treated with pemetrexed, pembrolizumab, and platinum.

Table 3: Laboratory Abnormalities Worsened from Baseline in ≥20% of Patients in KEYNOTE-189
 | Pemetrexed Pembrolizumab Platinum Chemotherapy |  | Placebo Pemetrexed Platinum Chemotherapy
Laboratory Testa | All Grades (%)b | Grade 3-4 (%) | All Grades (%) | Grade 3-4 (%)
Chemistry
Hyperglycemia | 63 | 9 | 60 | 7
Increased ALT | 47 | 3.8 | 42 | 2.6
Increased AST | 47 | 2.8 | 40 | 1.0
Hypoalbuminemia | 39 | 2.8 | 39 | 1.1
Increased creatinine | 37 | 4.2 | 25 | 1.0
Hyponatremia | 32 | 7 | 23 | 6
Hypophosphatemia | 30 | 10 | 28 | 14
Increased alkaline phosphatase | 26 | 1.8 | 29 | 2.1
Hypocalcemia | 24 | 2.8 | 17 | 0.5
Hyperkalemia | 24 | 2.8 | 19 | 3.1
Hypokalemia | 21 | 5 | 20 | 5
Hematology
Anemia | 85 | 17 | 81 | 18
Lymphopenia | 64 | 22 | 64 | 25
Neutropenia | 48 | 20 | 41 | 19
Thrombocytopenia | 30 | 12 | 29 | 8
a. Each test incidence is based on the number of patients who had both baseline and at least one on-study laboratory measurement available: pemetrexed/pembrolizumab/platinum chemotherapy (range: 381 to 401 patients) and placebo/pemetrexed/platinum chemotherapy (range: 184 to 197 patients).
b. Graded per NCI CTCAE version 4.03.

Initial Treatment in Combination with Cisplatin
The safety of pemetrexed was evaluated in Study JMDB, a randomized (1:1), open-label, multicenter trial conducted in chemotherapy-naive patients with locally advanced or metastatic NSCLC. Patients received either pemetrexed 500 mg/m^2 intravenously in combination with cisplatin 75 mg/m^2 intravenously on Day 1 of each 21-day cycle (n=839) or gemcitabine 1250 mg/m^2 intravenously on Days 1 and 8 in combination with cisplatin 75 mg/m^2 intravenously on Day 1 of each 21-day cycle (n=830). All patients were fully supplemented with folic acid and vitamin B12.

Study JMDB excluded patients with an Eastern Cooperative Oncology Group Performance Status (ECOG PS of 2 or greater), uncontrolled third-space fluid retention, inadequate bone marrow reserve and organ function, or a calculated creatinine clearance less than 45 mL/min. Patients unable to stop using aspirin or other non-steroidal anti-inflammatory drugs or unable to take folic acid, vitamin B12 or corticosteroids were also excluded from the study.

The data described below reflect exposure to pemetrexed plus cisplatin in 839 patients in Study JMDB. Median age was 61 years (range 26-83 years); 70% of patients were men; 78% were White, 16% were Asian, 2.9% were Hispanic or Latino, 2.1% were Black or African American, and < 1% were other races; 36% had an ECOG PS 0. Patients received a median of 5 cycles of pemetrexed.

Table 4 provides the frequency and severity of adverse reactions that occurred in ≥ 5% of 839 patients receiving pemetrexed in combination with cisplatin in Study JMDB. Study JMDB was not designed to demonstrate a statistically significant reduction in adverse reaction rates for pemetrexed, as compared to the control arm, for any specified adverse reaction listed in Table 4.

Table 4: Adverse Reactions Occurring in ≥ 5% of Fully Vitamin-Supplemented Patients Receiving Pemetrexed in Combination with Cisplatin in Study JMDB
Adverse Reactiona | Pemetrexed/Cisplatin (N=839) |  | Gemcitabine/Cisplatin (N=830)
Adverse Reactiona | All Grades (%) | Grade 3-4 (%) | All Grades (%) | Grade 3-4 (%)
All Adverse Reactions | 90 | 37 | 91 | 53
Laboratory
Hematologic
Anemia | 33 | 6 | 46 | 10
Neutropenia | 29 | 15 | 38 | 27
Thrombocytopenia | 10 | 4 | 27 | 13
Renal
Elevated creatinine | 10 | 1 | 7 | 1
Clinical
Gastrointestinal
Nausea | 56 | 7 | 53 | 4
Vomiting | 40 | 6 | 36 | 6
Anorexia | 27 | 2 | 24 | 1
Constipation | 21 | 1 | 20 | 0
Stomatitis/Pharyngitis | 14 | 1 | 12 | 0
Diarrhea | 12 | 1 | 13 | 2
Dyspepsia/Heartburn | 5 | 0 | 6 | 0
Constitutional Symptoms
Fatigue | 43 | 7 | 45 | 5
Dermatology/Skin
Alopecia | 12 | 0 | 21 | 1
Rash/Desquamation | 7 | 0 | 8 | 1
Neurology
Sensory neuropathy | 9 | 0 | 12 | 1
Taste disturbance | 8 | 0 | 9 | 0
a NCI CTCAE version 2.0.

The following additional adverse reactions of pemetrexed were observed.

Incidence 1% to < 5%
Body as a Whole — febrile neutropenia, infection, pyrexia
General Disorders— dehydration
Metabolism and Nutrition— increased AST, increased ALT
Renal — renal failure
Eye Disorder — conjunctivitis

Incidence < 1%
Cardiovascular — arrhythmia
General Disorders — chest pain
Metabolism and Nutrition — increased GGT
Neurology — motor neuropathy

Maintenance Treatment Following First-line Non-Pemetrexed Containing Platinum-Based Chemotherapy
The safety of pemetrexed was evaluated in Study JMEN, a randomized (2:1), placebo-controlled, multicenter trial conducted in patients with non-progressive locally advanced or metastatic NSCLC following four cycles of a first-line, platinum-based chemotherapy regimen. Patients received either pemetrexed 500 mg/m^2 or matching placebo intravenously every 21 days until disease progression or unacceptable toxicity. Patients in both study arms were fully supplemented with folic acid and vitamin B12.

Study JMEN excluded patients with an ECOG PS of 2 or greater, uncontrolled third-space fluid retention, inadequate bone marrow reserve and organ function or a calculated creatinine clearance < 45 mL/min. Patients unable to stop using aspirin or other non-steroidal anti-inflammatory drugs or unable to take folic acid, vitamin B12 or corticosteroids were also excluded from the study.

The data described below reflect exposure to pemetrexed in 438 patients in Study JMEN. Median age was 61 years (range 26-83 years), 73% of patients were men; 65% were White, 31% were Asian, 2.9% were Hispanic or Latino, and < 2% were other races; 39% had an ECOG PS 0. Patients received a median of 5 cycles of pemetrexed and a relative dose intensity of pemetrexed of 96%. Approximately half the patients (48%) completed at least six 21-day cycles and 23% completed ten or more 21-day cycles of pemetrexed.

Table 5 provides the frequency and severity of adverse reactions reported in ≥ 5% of the 438 pemetrexed-treated patients in Study JMEN.

Table 5: Adverse Reactions Occurring in ≥ 5% Fully Supplemented Patients Receiving Pemetrexed in Study JMEI
Adverse Reactiona | Pemetrexed (N=438) |  | Placebo (N=218)
Adverse Reactiona | All Grades (%) | Grade 3-4 (%) | All Grades (%) | Grade 3-4 (%)
All adverse reactions | 66 | 16 | 37 | 4
Laboratory
Hematologic
Anemia | 15 | 3 | 6 | 1
Neutropenia | 6 | 3 | 0 | 0
Hepatic
Increased ALT | 10 | 0 | 4 | 0
Increased AST | 8 | 0 | 4 | 0
Clinical
Constitutional Symptoms
Fatigue | 25 | 5 | 11 | 1
Gastrointestinal
Nausea | 19 | 1 | 6 | 1
Anorexia | 19 | 2 | 5 | 0
Vomiting | 9 | 0 | 1 | 0
Mucositis/Stomatitis | 7 | 1 | 2 | 0
Diarrhea | 5 | 1 | 3 | 0
Dermatology/Skin
Rash/Desquamation | 10 | 0 | 3 | 0
Neurology
Sensory neuropathy | 9 | 1 | 4 | 0
Infection | 5 | 2 | 2 | 0
a NCI CTCAE version 3.0.

The requirement for transfusions (9.5% versus 3.2%), primarily red blood cell transfusions, and for erythropoiesis stimulating agents (5.9% versus 1.8%) were higher in the pemetrexed arm compared to the placebo arm.

The following additional adverse reactions were observed in patients who received pemetrexed.

Incidence 1% to < 5%
Dermatology/Skin — alopecia, pruritis/itching
Gastrointestinal — constipation
General Disorders — edema, fever
Hematologic — thrombocytopenia
Eye Disorder — ocular surface disease (including conjunctivitis), increased lacrimation

Incidence < 1%
Cardiovascular — supraventricular arrhythmia
Dermatology/Skin — erythema multiforme
General Disorders — febrile neutropenia, allergic reaction/hypersensitivity
Neurology — motor neuropathy
Renal — renal failure

Maintenance Treatment Following First-line Pemetrexed Plus Platinum Chemotherapy
The safety of pemetrexed was evaluated in PARAMOUNT, a randomized (2:1), placebo-controlled study conducted in patients with non-squamous NSCLC with non-progressive (stable or responding disease) locally advanced or metastatic NSCLC following four cycles of pemetrexed in combination with cisplatin as first-line therapy for NSCLC. Patients were randomized to receive pemetrexed 500 mg/m^2 or matching placebo intravenously on Day 1 of each 21-day cycle until disease progression or unacceptable toxicity. Patients in both study arms received folic acid and vitamin B12 supplementation.

PARAMOUNT excluded patients with an ECOG PS of 2 or greater, uncontrolled third-space fluid retention, inadequate bone marrow reserve and organ function, or a calculated creatinine clearance < 45 mL/min. Patients unable to stop using aspirin or other non-steroidal anti-inflammatory drugs or unable to take folic acid, vitamin B12 or corticosteroids were also excluded from the study.

The data described below reflect exposure to pemetrexed in 333 patients in PARAMOUNT. Median age was 61 years (range 32 to 83 years); 58% of patients were men; 94% were White, 4.8% were Asian, and < 1% were Black or African American; 36% had an ECOG PS 0. The median number of maintenance cycles was 4 for pemetrexed and placebo arms.

Dose reductions for adverse reactions occurred in 3.3% of patients in the pemetrexed arm and 0.6% in the placebo arm. Dose delays for adverse reactions occurred in 22% of patients in the pemetrexed arm and 16% in the placebo arm.

Table 6 provides the frequency and severity of adverse reactions reported in ≥ 5% of the 333 pemetrexed-treated patients in PARAMOUNT.

Table 6: Adverse Reactions Occurring in ≥ 5% of Patients Receiving Pemetrexed in PARAMOUNT
Adverse Reactiona | Pemetrexed (N=333) |  | Cisplatin (N=167)
Adverse Reactiona | All Grades (%) | Grade 3-4 (%) | All Grades (%) | Grade 3-4 (%)
All Adverse Reactions | 53 | 17 | 34 | 4.8
Laboratory
Hematologic
Anemia | 15 | 4.8 | 4.8 | 0.6
Neutropenia | 9 | 3.9 | 0.6 | 0
Clinical
Constitutional Symptoms
Fatigue | 18 | 4.5 | 11 | 0.6
Gastrointestinal
Nausea | 12 | 0.3 | 2.4 | 0
Vomiting | 6 | 0 | 1.8 | 0
Mucositis/Stomatitis | 5 | 0.3 | 2.4 | 0
General Disorders
Edema | 5 | 0 | 3.6 | 0
a NCI CTCAE version 3.0.

The requirement for red blood cell (13% versus 4.8%) and platelet (1.5% versus 0.6%) transfusions, erythropoiesis stimulating agents (12% versus 7%), and granulocyte colony stimulating factors (6% versus 0%) were higher in the pemetrexed arm compared to the placebo arm.

The following additional Grade 3 or 4 adverse reactions were observed more frequently in the pemetrexed arm.

Incidence 1% to < 5%
Blood/Bone Marrow — thrombocytopenia
General Disorders — febrile neutropenia

Incidence < 1%
Cardiovascular — ventricular tachycardia, syncope
General Disorders — pain
Gastrointestinal — gastrointestinal obstruction
Neurologic — depression
Renal — renal failure
Vascular — pulmonary embolism

Treatment of Recurrent Disease After Prior Chemotherapy
The safety of pemetrexed was evaluated in Study JMEI, a randomized (1:1), open-label, active-controlled trial conducted in patients who had progressed following platinum-based chemotherapy. Patients received pemetrexed 500 mg/m^2 intravenously or docetaxel 75 mg/m^2 intravenously on Day 1 of each 21-day cycle. All patients on the pemetrexed arm received folic acid and vitamin B12 supplementation.

Study JMEI excluded patients with an ECOG PS of 3 or greater, uncontrolled third-space fluid retention, inadequate bone marrow reserve and organ function, or a calculated creatinine clearance < 45 mL/min. Patients unable to discontinue aspirin or other non-steroidal anti-inflammatory drugs or unable to take folic acid, vitamin B12 or corticosteroids were also excluded from the study.

The data described below reflect exposure to pemetrexed in 265 patients in Study JMEI. Median age was 58 years (range 22 to 87 years); 73% of patients were men; 70% were White, 24% were Asian, 2.6% were Black or African American, 1.8% were Hispanic or Latino, and < 2% were other races; 19% had an ECOG PS 0.

Table 7 provides the frequency and severity of adverse reactions reported in ≥ 5% of the 265 pemetrexed-treated patients in Study JMEI. Study JMEI is not designed to demonstrate a statistically significant reduction in adverse reaction rates for pemetrexed, as compared to the control arm, for any specified adverse reaction listed in Table 7 below.

Table 7: Adverse Reactions Occurring in ≥ 5% Fully Supplemented Patients Receiving Pemetrexed in Study JMEI
Adverse Reactiona | Pemetrexed (N=265) |  | Docetaxel (N=276)
Adverse Reactiona | All Grades (%) | Grade 3-4 (%) | All Grades (%) | Grade 3-4 (%)
Laboratory
Hematologic
Anemia | 19 | 4 | 22 | 4
Neutropenia | 11 | 5 | 45 | 40
Thrombocytopenia | 8 | 2 | 1 | 0
Hepatic
Increased ALT | 8 | 2 | 1 | 0
Increased AST | 7 | 1 | 1 | 0
Clinical
Constitutional Symptoms
Fatigue | 34 | 5 | 36 | 5
Fever | 8 | 0 | 8 | 0
Gastrointestinal
Nausea | 31 | 3 | 17 | 2
Anorexia | 22 | 2 | 24 | 3
Vomiting | 16 | 2 | 12 | 1
Stomatitis/Pharyngitis | 15 | 1 | 17 | 1
Diarrhea | 13 | 0 | 24 | 3
Constipation | 6 | 0 | 4 | 0
Dermatology/Skin
Rash/Desquamation | 14 | 0 | 6 | 0
Pruritis | 7 | 0 | 2 | 0
Alopecia | 6 | 1 | 38 | 2
a NCI CTCAE version 2.0.

The following additional adverse reactions were observed in patients assigned to receive pemetrexed.

Incidence 1% to < 5%
Body as a Whole — abdominal pain, allergic reaction/hypersensitivity, febrile neutropenia, infection
Dermatology/Skin — erythema multiforme
Neurology — motor neuropathy, sensory neuropathy

Incidence < 1%
Cardiovascular — supraventricular arrhythmias
Renal — renal failure

Mesothelioma

The safety of pemetrexed was evaluated in Study JMCH, a randomized (1:1), single-blind study conducted in patients with MPM who had received no prior chemotherapy for MPM. Patients received pemetrexed 500 mg/m^2 intravenously in combination with cisplatin 75 mg/m^2 intravenously on Day 1 of each 21-day cycle or cisplatin 75 mg/m^2 intravenously on Day 1 of each 21-day cycle administered until disease progression or unacceptable toxicity. Safety was assessed in 226 patients who received at least one dose of pemetrexed in combination with cisplatin and 222 patients who received at least one dose of cisplatin alone. Among 226 patients who received pemetrexed in combination with cisplatin, 74% (n=168) received full supplementation with folic acid and vitamin B12 during study therapy, 14% (n=32) were never supplemented, and 12% (n=26) were partially supplemented.

Study JMCH excluded patients with Karnofsky Performance Scale (KPS) of less than 70, inadequate bone marrow reserve and organ function, or a calculated creatinine clearance < 45 mL/min. Patients unable to stop using aspirin or other non-steroidal anti-inflammatory drugs were also excluded from the study.

The data described below reflect exposure to pemetrexed in 168 patients that were fully supplemented with folic acid and vitamin B12. Median age was 60 years (range 19 to 85 years); 82% were men; 92% were White, 5% were Hispanic or Latino, 3.0% were Asian, and < 1% were other races; 54% had KPS of 90-100. The median number of treatment cycles administered was 6 in the pemetrexed/cisplatin fully supplemented group and 2 in the pemetrexed/cisplatin never supplemented group. Patients receiving pemetrexed in the fully supplemented group had a relative dose intensity of 93% of the protocol-specified pemetrexed dose intensity. The most common adverse reaction resulting in dose delay was neutropenia.

Table 8 provides the frequency and severity of adverse reactions ≥ 5% in the subgroup of pemetrexed-treated patients who were fully vitamin supplemented in Study JMCH. Study JMCH was not designed to demonstrate a statistically significant reduction in adverse reaction rates for pemetrexed, as compared to the control arm, for any specified adverse reaction listed in the table below.

Table 8: Adverse Reactions Occurring in ≥ 5% Fully Supplemented Subgroup Patients Receiving Pemetrexed/Cisplatin in Study JMCHa
Adverse Reactionb | Pemetrexed/Cisplatin (N=168) |  | Cisplatin (N=163)
Adverse Reactionb | All Grades (%) | Grade 3-4 (%) | All Grades (%) | Grade 3-4 (%)
Laboratory
Hematologic
Neutropenia | 56 | 23 | 13 | 3
Anemia | 26 | 4 | 10 | 0
Thrombocytopenia | 23 | 5 | 9 | 0
Renal
Decreased creatinine clearance | 16 | 1 | 18 | 2
Elevated creatinine | 11 | 1 | 10 | 1
Clinical
Gastrointestinal
Nausea | 82 | 12 | 77 | 6
Vomiting | 57 | 11 | 50 | 4
Stomatitis/Pharyngitis | 23 | 3 | 6 | 0
Anorexia | 20 | 1 | 14 | 1
Diarrhea | 17 | 4 | 8 | 0
Constipation | 12 | 1 | 7 | 1
Dyspepsia | 5 | 1 | 1 | 0
Constitutional Symptoms
Fatigue | 48 | 10 | 42 | 9
Dermatology/Skin
Rash | 16 | 1 | 5 | 0
Alopecia | 11 | 0 | 6 | 0
Neurology
Sensory neuropathy | 10 | 0 | 10 | 1
Taste disturbance | 8 | 0 | 6 | 0
Metabolism and Nutrition
Dehydration | 7 | 4 | 1 | 1
Eye Disorder
Conjunctivitis | 5 | 0 | 1 | 0
a In Study JMCH, 226 patients received at least one dose of pemetrexed in combination with cisplatin and 222 patients received at least one dose of cisplatin. Table 8 provides the ADRs for subgroup of patients treated with pemetrexed in combination with cisplatin (168 patients) or cisplatin alone (163 patients) who received full supplementation with folic acid and vitamin B12 during study therapy.
b NCI CTCAE version 2.0

The following additional adverse reactions were observed in patients receiving pemetrexed plus cisplatin.

Incidence 1% to < 5%
Body as a Whole — febrile neutropenia, infection, pyrexia
Dermatology/Skin — urticaria
General Disorders — chest pain
Metabolism and Nutrition — increased AST, increased ALT, increased GGT
Renal — renal failure

Incidence < 1%
Cardiovascular — arrhythmia
Neurology — motor neuropathy

Exploratory Subgroup Analyses based on Vitamin Supplementation
Table 9 provides the results of exploratory analyses of the frequency and severity of NCI CTCAE Grade 3 or 4 adverse reactions reported in more pemetrexed-treated patients who did not receive vitamin supplementation (never supplemented) as compared with those who received vitamin supplementation with daily folic acid and vitamin B12 from the time of enrollment in Study JMCH (fully-supplemented).

Table 9: Exploratory Subgroup Analysis of Selected Grade 3-4 Adverse Reactions Occurring in Patients Receiving Pemetrexed in Combination with Cisplatin with or without Full Vitamin Supplementation in Study JMCHa
Grade 3-4 Adverse Reaction | Fully Supplemented Patients (N=168) | Never Supplemented Patients (N=32)
Neutropenia | 23 | 38
Vomiting | 11 | 31
Thrombocytopenia | 5 | 9
Diarrhea | 4 | 9
Febrile neutropenia | 1 | 9
Infection with Grade 3-4 neutropenia | 0 | 6
a NCI CTCAE version 2.0

The following adverse reactions occurred more frequently in patients who were fully vitamin supplemented than in patients who were never supplemented:

- hypertension (11% versus 3%)
- chest pain (8% versus 6%)
- thrombosis/embolism (6% versus 3%)

Additional Experience Across Clinical Trials
Sepsis, with or without neutropenia, including fatal cases: 1%
Severe esophagitis, resulting in hospitalization: less than 1%

6.2 Postmarketing Experience

The following adverse reactions have been identified during postapproval use of pemetrexed. Because these reactions are reported voluntarily from a population of uncertain size, it is not always possible to reliably estimate their frequency or establish a causal relationship to drug exposure.

Blood and Lymphatic System — immune-mediated hemolytic anemia
Gastrointestinal — colitis, pancreatitis
General Disorders and Administration Site Conditions — edema
Injury, poisoning, and procedural complications — radiation recall
Respiratory — interstitial pneumonitis
Skin — Serious and fatal bullous skin conditions, Stevens-Johnson syndrome, and toxic epidermal necrolysis

7 DRUG INTERACTIONS

7.1 Effect of Other Drugs on Pemetrexed

Ibuprofen

Ibuprofen increases exposure (AUC) of pemetrexed [see Clinical Pharmacology (12.3)]. In patients with creatinine clearance between 45 mL/min and 79 mL/min:

- Avoid administration of ibuprofen for 2 days before, the day of, and 2 days following administration of PEMFEXY [see Dosage and Administration (2.5)].
- Monitor patients more frequently for myelosuppression, renal, and gastrointestinal toxicity, if concomitant administration of ibuprofen cannot be avoided.

8 USE IN SPECIFIC POPULATIONS

8.1 Pregnancy

Risk Summary

Based on findings from animal studies and its mechanism of action, pemetrexed can cause fetal harm when administered to a pregnant woman [see Clinical Pharmacology (12.1)]. There are no available data on pemetrexed use in pregnant women. In animal reproduction studies, intravenous administration of pemetrexed to pregnant mice during the period of organogenesis was teratogenic, resulting in developmental delays and malformations at doses lower than the recommended human dose of 500 mg/m^2 (see Data). Advise pregnant women of the potential risk to a fetus [see use in Specific Population (8.3)].

In the U.S. general population, the estimated background risk of major birth defects and miscarriage in clinically recognized pregnancies is 2 to 4% and 15 to 20%, respectively.

Data

Animal Data
Pemetrexed was teratogenic in mice. Daily dosing of pemetrexed by intravenous injection to pregnant mice during the period of organogenesis increased the incidence of fetal malformations (cleft palate; protruding tongue; enlarged or misshaped kidney; and fused lumbar vertebra) at doses (based on BSA) 0.03 times the human dose of 500 mg/m^2. At doses, based on BSA, greater than or equal to 0.0012 times the 500 mg/m^2 human dose, pemetrexed administration resulted in dose-dependent increases in developmental delays (incomplete ossification of talus and skull bone; and decreased fetal weight).

8.2 Lactation

Risk Summary

There is no information regarding the presence of pemetrexed or its metabolites in human milk, the effects on the breastfed child, or the effects on milk production. Because of the potential for serious adverse reactions in a breastfed child from PEMFEXY, advise women not to breastfeed during treatment with PEMFEXY and for one week after the last dose.

8.3 Females and Males of Reproductive Potential

Based on animal data, pemetrexed can cause malformations and developmental delays when administered to a pregnant woman [see Use in Specific Populations (8.1)].

Pregnancy Testing
Verify pregnancy status of females of reproductive potential prior to initiating PEMFEXY [see Use in Specific Populations (8.1)].

Contraception
Females
Because of the potential for genotoxicity, advise females of reproductive potential to use effective contraception during treatment with PEMFEXY and for 6 months after the last dose.

Males
Because of the potential for genotoxicity, advise males with female partners of reproductive potential to use effective contraception during treatment with PEMFEXY and for 3 months after the last dose [see Nonclinical Toxicology (13.1)].

Infertility
Males
PEMFEXY may impair fertility in males of reproductive potential. It is not known whether these effects on fertility are reversible [see Nonclinical Toxicology (13.1)].

8.4 Pediatric Use

The safety and effectiveness of PEMFEXY in pediatric patients have not been established.

The safety and pharmacokinetics of pemetrexed were evaluated in two clinical studies conducted in pediatric patients with recurrent solid tumors (NCT00070473 N=32 and NCT00520936 N=72). Patients in both studies received concomitant vitamin B12 and folic acid supplementation and dexamethasone.

No tumor responses were observed. Adverse reactions observed in pediatric patients were similar to those observed in adults.

Single-dose pharmacokinetics of pemetrexed were evaluated in 22 patients age 4 to 18 years enrolled in NCT00070473 were within range of values in adults.

8.5 Geriatric Use

Of the 3,946 patients enrolled in clinical studies of pemetrexed, 34% were 65 and over and 4% were 75 and over. No overall differences in effectiveness were observed between these patients and younger patients. The incidences of Grade 3-4 anemia, fatigue, thrombocytopenia, hypertension, and neutropenia were higher in patients 65 years of age and older as compared to younger patients in at least one of five randomized clinical trials [see Adverse Reactions (6.1) and Clinical Studies (14.1, 14.2)].

8.6 Renal Impairment

Pemetrexed is primarily excreted by the kidneys. Decreased renal function results in reduced clearance and greater exposure (AUC) to pemetrexed compared with patients with normal renal function [see Warnings and Precautions (5.2, 5.6) and Clinical Pharmacology (12.3)]. No dosage is recommended for patients with creatinine clearance less than 45 mL/min [see Dosage and Administration (2.3)].

10 OVERDOSAGE

No drugs are approved for the treatment of pemetrexed overdose. Based on animal studies, administration of leucovorin may mitigate the toxicities of pemetrexed overdosage. It is not known whether pemetrexed is dialyzable.

11 DESCRIPTION

Pemetrexed is a folate analog metabolic inhibitor. Pemetrexed diacid, the drug substance, has the chemical name N-[4-[2-(2-amino-4,7-dihydro-4-oxo-1H-pyrrolo[2,3-d]pyrimidin-5-yl)ethyl]benzoyl]-L-glumatic acid. The molecular formula is C20H21N5O6 and the molecular weight is 427.41. The structural formula is as follows:

PEMFEXY (pemetrexed injection) for intravenous use is a sterile, clear, colorless to yellow or green-yellow solution . Each mL contains: 25 mg pemetrexed diacid, 260 mg propylene glycol, up to 16.5-19.9 mg tromethamine, and water for injection. Additional tromethamine not exceeding 19.9 mg/mL and/or hydrochloric acid may be added for pH adjustment.

12 CLINICAL PHARMACOLOGY

12.1 Mechanism of Action

Pemetrexed is a folate analog metabolic inhibitor that disrupts folate-dependent metabolic processes essential for cell replication. In vitro studies show that pemetrexed inhibits thymidylate synthase (TS), dihydrofolate reductase (DHFR), and glycinamide ribonucleotide formyltransferase (GARFT), which are folate-dependent enzymes involved in the de novo biosynthesis of thymidine and purine nucleotides. Pemetrexed is taken into cells by membrane carriers, such as the reduced folate carrier and membrane folate binding protein transport systems. Once in the cell, pemetrexed is converted to polyglutamate forms by the enzyme folylpolyglutamate synthetase. The polyglutamate forms are retained in cells and are inhibitors of TS and GARFT.

12.2 Pharmacodynamics

Pemetrexed inhibited the in vitro growth of mesothelioma cell lines (MSTO-211H, NCI-H2052) and showed synergistic effects when combined with cisplatin.

Based on population pharmacodynamic analyses, the depth of the absolute neutrophil counts (ANC) nadir correlates with the systemic exposure to pemetrexed and supplementation with folic acid and vitamin B12. There is no cumulative effect of pemetrexed exposure on ANC nadir over multiple treatment cycles.

12.3 Pharmacokinetics

Absorption

The pharmacokinetics of pemetrexed administered as a single-agent in doses ranging from 0.2 mg/m^2 to 838 mg/m^2 infused over a 10-minute period have been evaluated in 426 patients with a variety of solid tumors. Pemetrexed total systemic exposure (AUC) and maximum plasma concentration (Cmax) increased proportionally with increase of dose. The pharmacokinetics of pemetrexed did not change over multiple treatment cycles.

Distribution

Pemetrexed has a steady-state volume of distribution of 16.1 L. In vitro studies indicated that pemetrexed is 81% bound to plasma proteins.

Elimination

The total systemic clearance of pemetrexed is 91.8 mL/min and the elimination half-life of pemetrexed is 3.5 hours in patients with normal renal function (creatinine clearance of 90 mL/min). As renal function decreases, the clearance of pemetrexed decreases and exposure (AUC) of pemetrexed increases.

Metabolism

Pemetrexed is not metabolized to an appreciable extent.

Excretion

Pemetrexed is primarily eliminated in the urine, with 70% to 90% of the dose recovered unchanged within the first 24 hours following administration. In vitro studies indicated that pemetrexed is a substrate of OAT3 (organic anion transporter 3), a transporter that is involved in the active secretion of pemetrexed.

Specific Populations

Age (26 to 80 years) and sex had no clinically meaningful effect on the systemic exposure of pemetrexed based on population pharmacokinetic analyses.

Racial Groups

The pharmacokinetics of pemetrexed were similar in Whites and Blacks or African Americans. Insufficient data are available for other racial groups.

Patients with Hepatic Impairment

Pemetrexed has not been formally studied in patients with hepatic impairment. No effect of elevated AST, ALT, or total bilirubin on the PK of pemetrexed was observed in clinical studies.

Patients with Renal Impairment

Pharmacokinetic analyses of pemetrexed included 127 patients with impaired renal function. Plasma clearance of pemetrexed decreases as renal function decreases, with a resultant increase in systemic exposure. Patients with creatinine clearances of 45, 50, and 80 mL/min had 65%, 54%, and 13% increases, respectively in systemic exposure (AUC) compared to patients with creatinine clearance of 100 mL/min [see Dosage and Administration (2.3) and Warnings and Precautions (5.2)].

Third-Space Fluid

The pemetrexed plasma concentrations in patients with various solid tumors with stable, mild to moderate third-space fluid were comparable to those observed in patients without third space fluid collections. The effect of severe third space fluid on pharmacokinetics is not known.

Drug Interaction Studies

Drugs Inhibiting OAT3 Transporter

Ibuprofen, an OAT3 inhibitor, administered at 400 mg four times a day decreased the clearance of pemetrexed and increased its exposure (AUC) by approximately 20% in patients with normal renal function (creatinine clearance > 80 mL/min).

In Vitro Studies

Pemetrexed is a substrate for OAT3. Ibuprofen, an OAT3 inhibitor inhibited the uptake of pemetrexed in OAT3-expressing cell cultures with an average [Iu]/IC50 ratio of 0.38. In vitro data predict that at clinically relevant concentrations, other NSAIDs (naproxen, diclofenac, celecoxib) would not inhibit the uptake of pemetrexed by OAT3 and would not increase the AUC of pemetrexed to a clinically significant extent [see Drug Interactions (7)].

Pemetrexed is a substrate for OAT4. In vitro, ibuprofen and other NSAIDs (naproxen, diclofenac, celecoxib) are not inhibitors of OAT4 at clinically relevant concentrations.

Aspirin

Aspirin, administered in low to moderate doses (325 mg every 6 hours), does not affect the pharmacokinetics of pemetrexed.

Cisplatin

Cisplatin does not affect the pharmacokinetics of pemetrexed and the pharmacokinetics of total platinum are unaltered by pemetrexed.

Vitamins

Neither folic acid nor vitamin B12 affect the pharmacokinetics of pemetrexed.

Drugs Metabolized by Cytochrome P450 Enzymes

In vitro studies suggest that pemetrexed does not inhibit the clearance of drugs metabolized by CYP3A, CYP2D6, CYP2C9, and CYP1A2.

13 NONCLINICAL TOXICOLOGY

13.1 Carcinogenesis, Mutagenesis, Impairment of Fertility

No carcinogenicity studies have been conducted with pemetrexed. Pemetrexed was clastogenic in an in vivo micronucleus assay in mouse bone marrow but was not mutagenic in multiple in vitro tests (Ames assay, Chinese Hamster Ovary cell assay).

Pemetrexed administered intraperitoneally at doses of ≥0.1 mg/kg/day to male mice (approximately 0.0006 times the recommended human dose based on BSA) resulted in reduced fertility, hypospermia, and testicular atrophy.

14 CLINICAL STUDIES

14.1 Non-Squamous NSCLC

Initial Treatment in Combination with Pembrolizumab and Platinum

The efficacy of pemetrexed in combination with pembrolizumab and platinum chemotherapy was investigated in Study KEYNOTE-189 (NCT02578680), a randomized, multicenter, double-blind, active-controlled trial conducted in patients with metastatic non-squamous NSCLC, regardless of PD-L1 tumor expression status, who had not previously received systemic therapy for metastatic disease and in whom there were no EGFR or ALK genomic tumor aberrations. Patients with autoimmune disease that required systemic therapy within 2 years of treatment; a medical condition that required immunosuppression; or who had received more than 30 Gy of thoracic radiation within the prior 26 weeks were ineligible. Randomization was stratified by smoking status (never versus former/current), choice of platinum (cisplatin versus carboplatin), and tumor PD-L1 status (TPS <1% [negative] versus TPS ≥1%). Patients were randomized (2:1) to one of the following treatment arms:

- Pemetrexed 500 mg/m^2, pembrolizumab 200 mg, and investigator’s choice of cisplatin 75 mg/m^2 or carboplatin AUC 5 mg/mL/min intravenously on Day 1 of each 21-day cycle for 4 cycles followed by pemetrexed 500 mg/m^2 and pembrolizumab 200 mg intravenously every 3 weeks. Pemetrexed was administered after pembrolizumab and prior to platinum chemotherapy on Day 1.
- Placebo, pemetrexed 500 mg/m^2, and investigator’s choice of cisplatin 75 mg/m^2 or carboplatin AUC 5 mg/mL/min intravenously on Day 1 of each 21-day cycle for 4 cycles followed by placebo and pemetrexed 500 mg/m^2 intravenously every 3 weeks.

Treatment with pemetrexed continued until RECIST v1.1 (modified to follow a maximum of 10 target lesions and a maximum of 5 target lesions per organ)-defined progression of disease as determined by the investigator or unacceptable toxicity. Patients randomized to placebo, pemetrexed, and platinum chemotherapy were offered pembrolizumab as a single agent at the time of disease progression.

Assessment of tumor status was performed at Week 6, Week 12, and then every 9 weeks thereafter. The main efficacy outcome measures were OS and PFS as assessed by BICR RECIST v1.1, modified to follow a maximum of 10 target lesions and a maximum of five target lesions per organ. Additional efficacy outcome measures were ORR and duration of response, as assessed by the BICR according to RECIST v1.1, modified to follow a maximum of 10 target lesions and a maximum of 5 target lesions per organ.

A total of 616 patients were randomized: 410 patients to the pemetrexed, pembrolizumab, and platinum chemotherapy arm and 206 to the placebo, pemetrexed, and platinum chemotherapy arm. The study population characteristics were: median age of 64 years (range: 34 to 84); 49% age 65 or older; 59% male; 94% White and 3% Asian; 56% ECOG performance status of 1; and 18% with history of brain metastases. Thirty-one percent had tumor PD-L1 expression TPS < 1%. Seventy-two percent received carboplatin and 12% were never smokers. A total of 85 patients in the placebo, pemetrexed, and chemotherapy arm received an anti-PD-1/PD-L1 monoclonal antibody at the time of disease progression.

The trial demonstrated a statistically significant improvement in OS and PFS for patients randomized to pemetrexed in combination with pembrolizumab and platinum chemotherapy compared with placebo, pemetrexed, and platinum chemotherapy (see Table 10 and Figure 1).

Table 10: Efficacy Results of KEYNOTE-189

Endpoint | Pemetrexed Pembrolizumab Platinum Chemotherapy n=410 | Placebo Pemetrexed Platinum Chemotherapy n=206
OS
Number (%) of patients with event | 127 (31%) | 108 (52%)
Median in months (95% CI) | NR (NR, NR) | 11.3 (8.7, 15.1)
Hazard ratioa (95% CI) | 0.49 (0.38, 0.64)
p-valueb | <0.0001
PFS
Number of patients with event (%) | 245 (60%) | 166 (81%)
Median in months (95% CI) | 8.8 (7.6, 9.2) | 4.9 (4.7, 5.5)
Hazard ratioa (95% CI) | 0.52 (0.43, 0.64)
p-valueb | <0.0001
ORR
Overall response ratec (95% CI) | 48% (43, 53) | 19% (14, 25)
Complete response | 0.005 | 0.005
Partial response | 47% | 18%
p-valued | <0.0001
Duration of Response
Median in months (range) | 11.2 (1.1+, 18.0+) | 7.8 (2.1+, 16.4+)
a Based on the stratified Cox proportional hazard model.
b Based on stratified log-rank test.
c Response: Best objective response as confirmed complete response or partial response.
d Based on Miettinen and Nurminen method stratified by PD-L1 status, platinum chemotherapy and smoking status.
NR = not reached

At the protocol specified final OS analysis, the median in the pemetrexed in combination with pembrolizumab and platinum chemotherapy arm was 22.0 months (95% CI: 19.5, 24.5) compared to 10.6 months (95% CI: 8.7, 13.6) in the placebo with pemetrexed and platinum chemotherapy arm, with an HR of 0.56 (95% CI: 0.46, 0.69).

Figure 1: Kaplan-Meier Curve for Overall Survival in KEYNOTE-189*

*Based on the protocol-specified final OS analysis

P+P+C = pemetrexed + pembrolizumab + platinum chemotherapy.

P+C = pemetrexed + platinum chemotherapy + placebo.

Initial Treatment in Combination with Cisplatin

The efficacy of pemetrexed was evaluated in Study JMDB (NCT00087711), a multi-center, randomized (1:1), open-label study conducted in 1725 chemotherapy-naive patients with Stage IIIb/IV NSCLC. Patients were randomized to receive pemetrexed with cisplatin or gemcitabine with cisplatin. Randomization was stratified by Eastern Cooperative Oncology Group Performance Status (ECOG PS 0 versus 1), sex, disease stage, basis for pathological diagnosis (histopathological/cytopathological), history of brain metastases, and investigative center. Pemetrexed was administered intravenously over 10 minutes at a dose of 500 mg/m^2 on Day 1 of each 21-day cycle and cisplatin was administered intravenously at a dose of 75 mg/m^2 approximately 30 minutes after pemetrexed administration on Day 1 of each cycle. Gemcitabine was administered at a dose of 1250 mg/m^2 on Day 1 and Day 8 of each 21-day cycle and cisplatin was administered intravenously at a dose of 75 mg/m^2 approximately 30 minutes after administration of gemcitabine on Day 1 of each cycle. Treatment was administered up to a total of 6 cycles; patients in both arms received folic acid, vitamin B12, and dexamethasone [see Dosage and Administration (2.4)]. The major efficacy outcome measure was overall survival.

A total of 1725 patients were enrolled with 862 patients randomized to pemetrexed in combination with cisplatin and 863 patients to gemcitabine in combination with cisplatin. The median age was 61 years (range 26-83 years), 70% were male, 78% were White, 17% were Asian, 2.9% were Hispanic or Latino, and 2.1% were Black or African American, and < 1% were other races. Among patients for whom ECOG PS (n=1722) and smoking history (n=1516) were collected, 65% had an ECOG PS of 1, 36% had an ECOG PS of 0, and 84% were smokers. For tumor characteristics, 73% had non-squamous NSCLC and 27% had squamous NSCLC; 76% had Stage IV disease. Among 1252 patients with non-squamous NSCLC histology, 68% had a diagnosis of adenocarcinoma, 12% had large cell histology and 20% had other histologic subtypes.

Efficacy results for Study JMDB are presented in Table 11 and Figure 2.

Table 11: Efficacy Results in Study JMDB
Efficacy Parameter | Pemetrexed/Cisplatin (N=862) | Gemcitabine/Cisplatin (N=863)
Overall Survival
Median (months) (95% CI) | 10.3 (9.8,11.2) | 10.3 (9.6,10.9)
Hazard ratio (HR)a,b (95% CI) | 0.94 (0.84,1.05)
Progression-Free Survival
Median (months) (95% CI) | 4.8 (4.6,5.3) | 5.1 (4.6,5.5)
Hazard ratio (HR)a, b (95% CI) | 1.04 (0.94,1.15)
Overall Response Rate (95% CI) | 27.1% (24.2%,30.1%) | 24.7% (21.8%,27.6%)
a Unadjusted for multiple comparisons.
b Adjusted for sex, stage, basis of diagnosis, and performance status

Figure 2: Kaplan-Meier Curves for Overall Survival in Study JMDB

In pre-specified analyses assessing the impact of NSCLC histology on overall survival, clinically relevant differences in survival according to histology were observed. These subgroup analyses are shown in Table 12 and Figure 3 and Figure 4. This difference in treatment effect for pemetrexed based on histology demonstrating a lack of efficacy in squamous cell histology was also observed in Studies JMEN and JMEI.

Table 12: Overall Survival by NSCLC Histologic Subgroup in Study JMDB
Histologic Subgroup | Pemetrexed/Cisplatin (N=862) | Gemcitabine/ Cisplatin (N=863)
Non-squamous NSCLC (N=1252)
Median (months) (95% CI) | 11.0 (10.1,12.5) | 10.1 (9.3,10.9)
Hazard ratio (HR)a,b (95% CI) | 0.84 (0.74,0.96)
Adenocarcinoma (N=847)
Median (months) (95% CI) | 12.6 (10.7,13.6) | 10.9 (10.2,11.9)
Hazard ratio (HR)a,b (95% CI) | 0.84 (0.71,0.99)
Large Cell (N=153)
Median (months) (95% CI) | 10.4 (8.6,14.1) | 6.7 (5.5,9.0)
Hazard ratio (HR)a,b (95% CI) | 0.67 (0.48,0.96)
Non-squamous, not otherwise specified (N=252)
Median (months) (95% CI) | 8.6 (6.8,10.2) | 9.2 (8.1,10.6)
Hazard ratio (HR)a,b (95% CI) | 1.08 (0.81,1.45)
Squamous Cell (N=473)
Median (months) (95% CI) | 9.4 (8.4,10.2) | 10.8 (9.5,12.1)
Hazard ratio (HR)a,b (95% CI) | 1.23 (1.00,1.51)
a Unadjusted for multiple comparisons.
b Adjusted for ECOG PS, sex, disease stage, and basis for pathological diagnosis (histopathological/cytopathological).

Figure 3: Kaplan-Meier Curves for Overall Survival in Non-Squamous NSCLC in Study JMDB

Figure 4: Kaplan-Meier Curves for Overall Survival in Squamous NSCLC in Study JMDB

Maintenance Treatment Following First-line Non-Pemetrexed Containing Platinum-Based Chemotherapy

The efficacy of pemetrexed as maintenance therapy following first-line platinum-based chemotherapy was evaluated in Study JMEN (NCT00102804), a multicenter, randomized (2:1), double-blind, placebo-controlled study conducted in 663 patients with Stage IIIb/IV NSCLC who did not progress after four cycles of platinum-based chemotherapy. Patients were randomized to receive pemetrexed 500 mg/m^2 intravenously every 21 days or placebo until disease progression or intolerable toxicity. Patients in both study arms received folic acid, vitamin B12 and dexamethasone [see Dosage and Administration (2.4)]. Randomization was carried out using a minimization approach [Pocock and Simon (1975)] using the following factors: sex, ECOG PS (0 versus 1), response to prior chemotherapy (complete or partial response versus stable disease), history of brain metastases (yes versus no), non-platinum component of induction therapy (docetaxel versus gemcitabine versus paclitaxel), and disease stage (IIIb versus IV). The major efficacy outcome measures were progression-free survival based on assessment by independent review and overall survival; both were measured from the date of randomization in Study JMEN.

A total of 663 patients were enrolled with 441 patients randomized to pemetrexed and 222 patients randomized to placebo. The median age was 61 years (range 26-83 years); 73% were male; 65% were White, 32% were Asian, 2.9% were Hispanic or Latino, and < 2% were other races; 60% had an ECOG PS of 1; and 73% were current or former smokers. Median time from initiation of platinum-based chemotherapy to randomization was 3.3 months (range 1.6 to 5.1 months) and 49% of the population achieved a partial or complete response to first-line, platinum-based chemotherapy. With regard to tumor characteristics, 81% had Stage IV disease, 73% had non-squamous NSCLC and 27% had squamous NSCLC. Among the 481 patients with non-squamous NSCLC, 68% had adenocarcinoma, 4% had large cell, and 28% had other histologies.

Efficacy results for Study JMEN are presented in Table 13 and Figure 5.

Table 13: Efficacy Results in Study JMEN
Efficacy Parameter | Pemetrexed | Placebo
Overall survival | N=441 | N=222
Median (months) (95% CI) | 13.4 (11.9,15.9) | 10.6 (8.7,12.0)
Hazard ratio (HR)a (95% CI) | 0.79 (0.65,0.95)
p-value | p=0.012
Progression-free survival per independent review | N=387 | N=194
Median (months) (95% CI) | 4.0 (3.1,4.4) | 2.0 (1.5,2.8)
Hazard ratio (HR)a (95% CI) | 0.60 (0.49,0.73)
p-value | p < 0.00001
a Hazard ratios are adjusted for multiplicity but not for stratification variables.

Figure 5: Kaplan-Meier Curves for Overall Survival in Study JMEN

The results of pre-specified subgroup analyses by NSCLC histology are presented in Table 14 and Figure 6 and Figure 7.

Table 14: Efficacy Results by NSCLC Histologic Subgroup in Study JMEN
Histologic Subgroup | Overall Survival |  | Progression-Free Survival Per Independent Review
Histologic Subgroup | Pemetrexed (N=441) | Placebo (N=222) | Pemetrexed (N=387) | Placebo (N=194)
Non-squamous NSCLC (n=481)
Median (months) | 15.5 | 10.3 | 4.4 | 1.8
Hazard ratio (HR)a (95% CI) | 0.70 (0.56,0.88) |  | 0.47 (0.37,0.60)
Adenocarcinoma (n=328)
Median (months) | 16.8 | 11.5 | 4.6 | 2.7
Hazard ratio (HR)a (95% CI) | 0.73 (0.56,0.96) |  | 0.51 (0.38,0.68)
Large cell carcinoma (n=20)
Median (months) | 8.4 | 7.9 | 4.5 | 1.5
Hazard ratio (HR)a (95% CI) | 0.98 (0.36,2.65) |  | 0.40 (0.12,1.29)
Otherb (n=133)
Median (months) | 11.3 | 7.7 | 4.1 | 1.6
Hazard ratio (HR)a (95% CI) | 0.61 (0.40,0.94) |  | 0.44 (0.28,0.68)
Squamous cell NSCLC (n=182)
Median (months) | 9.9 | 10.8 | 2.4 | 2.5
Hazard ratio (HR)a (95% CI) | 1.07 (0.77,1.50) |  | 1.03 (0.71,1.49)
a Hazard ratios are not adjusted for multiplicity.
b Primary diagnosis of NSCLC not specified as adenocarcinoma, large cell carcinoma, or squamous cell carcinoma.

Figure 6: Kaplan-Meier Curves for Overall Survival in Non-Squamous NSCLC in Study JMEN

Figure 7: Kaplan-Meier Curves for Overall Survival in Squamous NSCLC in Study JMEN

Maintenance Treatment Following First-line Pemetrexed Plus Platinum Chemotherapy

The efficacy of pemetrexed as maintenance therapy following first-line platinum-based chemotherapy was also evaluated in PARAMOUNT (NCT00789373), a multi-center, randomized (2:1), double-blind, placebo-controlled study conducted in patients with Stage IIIb/IV non-squamous NSCLC who had completed four cycles of pemetrexed in combination with cisplatin and achieved a complete response (CR) or partial response (PR) or stable disease (SD). Patients were required to have an ECOG PS of 0 or 1. Patients were randomized to receive pemetrexed 500 mg/m^2 intravenously every 21 days or placebo until disease progression. Randomization was stratified by response to pemetrexed in combination with cisplatin induction therapy (CR or PR versus SD), disease stage (IIIb versus IV), and ECOG PS (0 versus 1). Patients in both arms received folic acid, vitamin B12, and dexamethasone. The main efficacy outcome measure was investigator-assessed progression-free survival (PFS) and an additional efficacy outcome measure was overall survival (OS); PFS and OS were measured from the time of randomization.

A total of 539 patients were enrolled with 359 patients randomized to pemetrexed and 180 patients randomized to placebo. The median age was 61 years (range 32 to 83 years); 58% were male; 95% were White, 4.5% were Asian, and < 1% were Black or African American; 67% had an ECOG PS of 1; 78% were current or former smokers; and 43% of the population achieved a partial or complete response to first-line, platinum-based chemotherapy. With regard to tumor characteristics, 91% had Stage IV disease, 87% had adenocarcinoma, 7% had large cell, and 6% had other histologies.

Efficacy results for PARAMOUNT are presented in Table 15 and Figure 8.

Table 15: Efficacy Results in PARAMOUNT
Efficacy Parameter | Pemetrexed (N=359) | Placebo (N=180)
Overall survival
Median (months) (95% CI) | 13.9 (12.8,16.0) | 11.0 (10.0,12.5)
Hazard ratio (HR)a (95% CI) | 0.78 (0.64,0.96)
p-value | p=0.02
Progression-free survivalb
Median (months) (95% CI) | 4.1 (3.2,4.6) | 2.8 (2.6,3.1)
Hazard ratio (HR)a (95% CI) | 0.62 (0.49,0.79)
p-value | p < 0.0001
a Hazard ratios are adjusted for multiplicity but not for stratification variables.
b Based on investigator's assessment.

Figure 8: Kaplan-Meier Curves for Overall Survival in PARAMOUNT

Treatment of Recurrent Disease After Prior Chemotherapy

The efficacy of pemetrexed was evaluated in Study JMEI (NCT00004881), a multicenter, randomized (1:1), open-label study conducted in patients with Stage III or IV NSCLC that had recurred or progressed following one prior chemotherapy regimen for advanced disease. Patients were randomized to receive pemetrexed 500 mg/m^2 intravenously or docetaxel 75 mg/m^2 as a 1-hour intravenous infusion once every 21 days. Patients randomized to pemetrexed also received folic acid and vitamin B12. The study was designed to show that overall survival with pemetrexed was non-inferior to docetaxel, as the major efficacy outcome measure, and that overall survival was superior for patients randomized to pemetrexed compared to docetaxel, as a secondary outcome measure.

A total of 571 patients were enrolled with 283 patients randomized to pemetrexed and 288 patients randomized to docetaxel. The median age was 58 years (range 22 to 87 years); 72% were male; 71% were White, 24% were Asian, 2.8% were Black or African American, 1.8% were Hispanic or Latino, and < 2% were other races; 88% had an ECOG PS of 0 or 1. With regard to tumor characteristics, 75% had Stage IV disease; 53% had adenocarcinoma, 30% had squamous histology; 8% large cell; and 9% had other histologic subtypes of NSCLC.

The efficacy results in the overall population and in subgroup analyses based on histologic subtype are provided in Table 16 and Table 17 , respectively. Study JMEI did not show an improvement in overall survival in the intent-to-treat population. In subgroup analyses, there was no evidence of a treatment effect on survival in patients with squamous NSCLC; the absence of a treatment effect in patients with squamous NSCLC was also observed Studies JMDB and JMEN [see Clinical Studies (14.1)].

Table 16: Efficacy Results in Study JMEI
Efficacy Parameter | Pemetrexed (N=283) | Docetaxel (N=288)
Overall survival
Median (months) (95% CI) | 8.3 (7.0,9.4) | 7.9 (6.3,9.2)
Hazard ratio (HR)a (95% CI) | 0.99 (0.82,1.20)
Progression-free survival
Median (months) (95% CI) | 2.9 (2.4,3.1) | 2.9 (2.7,3.4)
Hazard ratio (HR)a (95% CI) | 0.97 (0.82,1.16)
Overall response rate (95% CI) | 8.5% (5.2%,11.7%) | 8.3% (5.1%,11.5%)
a Hazard ratios are not adjusted for multiplicity or for stratification variables.

Table 17: Exploratory Efficacy Analyses by Histologic Subgroup in Study JMEI
Histologic Subgroup | Pemetrexed (N=283) | Docetaxel (N=288)
Non-squamous NSCLC (N=399)
Median (months) (95% CI) | 9.3 (7.8,9.7) | 8.0 (6.3,9.3)
Hazard ratio (HR)a (95% CI) | 0.89 (0.71,1.13)
Adenocarcinoma (N=301)
Median (months) (95% CI) | 9.0 (7.6,9.6) | 9.2 (7.5,11.3)
Hazard ratio (HR)a (95% CI) | 1.09 (0.83,1.44)
Large Cell (N=47)
Median (months) (95% CI) | 12.8 (5.8,14.0) | 4.5 (2.3,9.1)
Hazard ratio (HR)a (95% CI) | 0.38 (0.18,0.78)
Otherb (N=51)
Median (months) (95% CI) | 9.4 (6.0,10.1) | 7.9 (4.0,8.9)
Hazard ratio (HR)a (95% CI) | 0.62 (0.32,1.23)
Squamous NSCLC (N=172)
Median (months) (95% CI) | 6.2 (4.9,8.0) | 7.4 (5.6,9.5)
Hazard ratio (HR)a (95% CI) | 1.32 (0.93,1.86)
a Hazard ratio unadjusted for multiple comparisons.
b Primary diagnosis of NSCLC not specified as adenocarcinoma, large cell carcinoma, or squamous cell carcinoma.

14.2 Mesothelioma

The efficacy of pemetrexed was evaluated in Study JMCH (NCT00005636), a multicenter, randomized (1:1), single-blind study conducted in patients with MPM who had received no prior chemotherapy. Patients were randomized (n=456) to receive pemetrexed 500 mg/m^2 intravenously over 10 minutes followed 30 minutes later by cisplatin 75 mg/m^2 intravenously over two hours on Day 1 of each 21-day cycle or to receive cisplatin 75 mg/m^2 intravenously over 2 hours on Day 1 of each 21-day cycle; treatment continued until disease progression or intolerable toxicity. The study was modified after randomization and treatment of 117 patients to require that all patients receive folic acid 350 mcg to 1000 mcg daily beginning 1 to 3 weeks prior to the first dose of pemetrexed and continuing until 1 to 3 weeks after the last dose, vitamin B12 1000 mcg intramuscularly 1 to 3 weeks prior to first dose of pemetrexed and every 9 weeks thereafter, and dexamethasone 4 mg orally, twice daily, for 3 days starting the day prior to each pemetrexed dose. Randomization was stratified by multiple baseline variables including KPS, histologic subtype (epithelial, mixed, sarcomatoid, other), and sex. The major efficacy outcome measure was overall survival and additional efficacy outcome measures were time to disease progression, overall response rate, and response duration.

A total of 448 patients received at least one dose of protocol-specified therapy; 226 patients were randomized to and received at least one dose of pemetrexed plus cisplatin, and 222 patients were randomized to and received cisplatin. Among the 226 patients who received cisplatin with pemetrexed, 74% received full supplementation with folic acid and vitamin B12 during study therapy, 14% were never supplemented, and 12% were partially supplemented. Across the study population, the median age was 61 years (range: 20 to 86 years); 81% were male; 92% were White, 5% were Hispanic or Latino, 3.1% were Asian, and < 1% were other races; and 54% had a baseline KPS score of 90-100% and 46% had a KPS score of 70-80%. With regard to tumor characteristics, 46% had Stage IV disease, 31% Stage III, 15% Stage II, and 7% Stage I disease at baseline; the histologic subtype of mesothelioma was epithelial in 68% of patients, mixed in 16%, sarcomatoid in 10% and other histologic subtypes in 6%. The baseline demographics and tumor characteristics of the subgroup of fully supplemented patients was similar to the overall study population.

The efficacy results from Study JMCH are summarized in Table 18 and Figure 9.

Table 18: Efficacy Results in Study JMCH
Efficacy Parameter | All Randomized and Treated Patients (N=448) |  | Fully Supplemented Patients (N=331)
Efficacy Parameter | Pemetrexed/ Cisplatin (N=226) | Cisplatin (N=222) | Pemetrexed/ Cisplatin (N=168) | Cisplatin (N=163)
Overall survival
Median (months) (95% CI) | 12.1 (10.0,14.4) | 9.3 (7.8,10.7) | 13.3 (11.4,14.9) | 10.0 (8.4,11.9)
Hazard ratio (HR)a | 0.77 |  | 0.75
Log rank p-value | 0.020 |  | NAb
a Hazard ratios are not adjusted for stratification variables.
b Not a pre-specified analysis.

Figure 9: Kaplan-Meier Curves for Overall Survival in Study JMCH

Based upon prospectively defined criteria (modified Southwest Oncology Group methodology), the objective tumor response rate for pemetrexed plus cisplatin was greater than the objective tumor response rate for cisplatin alone. There was also improvement in lung function (forced vital capacity) in the pemetrexed plus cisplatin arm compared to the control arm.

15 REFERENCES

1. “OSHA Hazardous Drugs.” OSHA. [http://www.osha.gov/hazardous-drugs]

16 HOW SUPPLIED/STORAGE AND HANDLING

PEMFEXY (pemetrexed injection) is a clear, colorless to yellow or green-yellow solution supplied in a multi-dose vial for intravenous use.

NDC 42367-531-33: Carton containing one (1) multi-dose vial of 500 mg/20 mL (25 mg/mL).

Store refrigerated at 2°C to 8°C (36°F to 46°F). Protect from light until time of use.

PEMFEXY is a hazardous drug. Follow applicable special handling and disposal procedures.^1

17 PATIENT COUNSELING INFORMATION

Advise the patient to read the FDA-approved patient labeling (Patient Information).

- Premedication and Concomitant Medication: Instruct patients to take folic acid as directed and to keep appointments for vitamin B12 injections to reduce the risk of treatment-related toxicity. Instruct patients of the requirement to take corticosteroids to reduce the risks of treatment-related toxicity [see Dosage and Administration (2.4) and Warnings and Precautions (5.1)].
- Myelosuppression: Inform patients of the risk of low blood cell counts and instruct them to immediately contact their physician for signs of infection, fever, bleeding, or symptoms of anemia [see Warnings and Precautions (5.1)].
- Renal Failure: Inform patients of the risks of renal failure, which may be exacerbated in patients with dehydration arising from severe vomiting or diarrhea. Instruct patients to immediately contact their healthcare provider for a decrease in urine output [see Warnings and Precautions (5.2)].
- Bullous and Exfoliative Skin Disorders: Inform patients of the risks of severe and exfoliative skin disorders. Instruct patients to immediately contact their healthcare provider for development of bullous lesions or exfoliation in the skin or mucous membranes [see Warnings and Precautions (5.3)].
- Interstitial Pneumonitis: Inform patients of the risks of pneumonitis. Instruct patients to immediately contact their healthcare provider for development of dyspnea or persistent cough [see Warnings and Precautions (5.4)].
- Radiation Recall:Inform patients who have received prior radiation of the risks of radiation recall. Instruct patients to immediately contact their healthcare provider for development of inflammation or blisters in an area that was previously irradiated [see Warnings and Precautions (5.5)].
- Increased Risk of Toxicity with Ibuprofen in Patients with Renal Impairment: Advise patients with mild to moderate renal impairment of the risks associated with concomitant ibuprofen use and instruct them to avoid use of all ibuprofen containing products for 2 days before, the day of, and 2 days following administration of PEMFEXY [see Dosage and Administration (2.5), Warnings and Precautions (5.6), and Drug Interactions (7)].
- Embryo-Fetal Toxicity:
  - Advise females of reproductive potential and males with female partners of reproductive potential of the potential risk to a fetus. Advise females to inform their healthcare provider of a known or suspected pregnancy [see Warnings and Precautions (5.4) and Use in Specific Populations (8.1)].
  - Advise females of reproductive potential to use effective contraception during treatment with PEMFEXY and for 6 months after the last dose [see Use in Specific Populations (8.3)].
  - Advise males with female partners of reproductive potential to use effective contraception during treatment with PEMFEXY and for 3 months after the last dose [see Use in Specific Populations (8.3), Nonclinical Toxicology (13.1)].
- Lactation: Advise women not to breastfeed during treatment with PEMFEXY and for 1 week after the last dose [see Use in Specific Populations (8.2)].

Marketed by:
Eagle Pharmaceuticals, Inc.
Woodcliff Lake, NJ 07677

PATIENT INFORMATION

PEMFEXY(Pem-FECKS-ee)
(pemetrexed injection)
for intravenous use

What is PEMFEXY?

PEMFEXY is a prescription medicine used to treat:

- a kind of lung cancer called non-squamous non-small cell lung cancer (NSCLC). PEMFEXY is used:
  - as the first treatment in combination with pembrolizumab and platinum chemotherapy when your lung cancer with no abnormal EGFR or ALK gene has spread (advanced NSCLC).
  - as the first treatment in combination with cisplatin when your lung cancer has spread (advanced NSCLC).
  - alone as maintenance treatment after you have received 4 cycles of chemotherapy that contains platinum for first treatment of your advanced NSCLC and your cancer has not progressed.
  - alone when your lung cancer has returned or spread after prior chemotherapy.

PEMFEXY is not for use for the treatment of people with squamous cell non-small cell lung cancer.

- a kind of cancer called malignant pleural mesothelioma. This cancer affects the lining of the lungs and chest wall. PEMFEXY is used in combination with cisplatin as the first treatment for malignant pleural mesothelioma that cannot be removed by surgery or you are not able to have surgery.

PEMFEXY has not been shown to be safe and effective in children.

Do not take PEMFEXY if you have had a severe allergic reaction to any medicine that contains pemetrexed.

Before taking PEMFEXY, tell your healthcare provider about all of your medical conditions, including if you:

- have kidney problems.
- have had radiation therapy.
- are pregnant or plan to become pregnant. PEMFEXY can harm your unborn baby.
  Females who are able to become pregnant:
  Your healthcare provider will check to see if you are pregnant before you start treatment with PEMFEXY.
  You should use effective birth control (contraception) during treatment with PEMFEXY and for 6 months after the last dose. Tell your healthcare provider right away if you become pregnant or think you are pregnant during treatment with PEMFEXY.
  Males with female partners who are able to become pregnant should use effective birth control (contraception) during treatment with PEMFEXY and for 3 months after the last dose.
- are breastfeeding or plan to breastfeed. It is not known if PEMFEXY passes into breast milk. Do not breastfeed during treatment with PEMFEXY and for 1 week after the last dose.

Tell your healthcare provider about all the medicines you take, including prescription and over-the-counter medicines, vitamins, and herbal supplements.

Tell your healthcare provider if you have kidney problems and take a medicine that contains ibuprofen. You should avoid taking ibuprofen for 2 days before, the day of, and 2 days after receiving treatment with PEMFEXY.

How is PEMFEXY given?

- It is very important to take folic acid and vitamin B12 during your treatment with PEMFEXY to lower your risk of harmful side effects.
  - Take folic acid exactly as prescribed by your healthcare provider 1 time a day, beginning 7 days (1 week) before your first dose of PEMFEXY and continue taking folic acid until 21 days (3 weeks) after your last dose of PEMFEXY.
  - Your healthcare provider will give you vitamin B12 injections during treatment with PEMFEXY. You will get your first vitamin B12 injection 7 days (1 week) before your first dose of PEMFEXY, and then every 3 cycles.
- Your healthcare provider will prescribe a medicine called corticosteroid for you to take 2 times a day for 3 days, beginning the day before each treatment with PEMFEXY.
- PEMFEXY is given to you by intravenous (IV) infusion into your vein. The infusion is given over 10 minutes.
- PEMFEXY is usually given 1 time every 21 days (3 weeks).

What are the possible side effects of PEMFEXY?

PEMFEXY can cause serious side effects, including:

- Low blood cell counts. Low blood cell counts can be severe, including low white blood cell counts (neutropenia), low platelet counts (thrombocytopenia), and low red blood cell counts (anemia). Your healthcare provider will do blood tests to check your blood cell counts regularly during your treatment with PEMFEXY. Tell your healthcare provider right away if you have any signs of infection, fever, bleeding, or severe tiredness during your treatment with PEMFEXY.
- Kidney problems, including kidney failure. PEMFEXY can cause severe kidney problems that can lead to death. Severe vomiting or diarrhea can lead to loss of fluids (dehydration) which may cause kidney problems to become worse. Tell your healthcare provider right away if you have a decrease in amount of urine.
- Severe skin reactions. Severe skin reactions that may lead to death can happen with PEMFEXY. Tell your healthcare provider right away if you develop blisters, skin sores, skin peeling, or painful sores, or ulcers in your mouth, nose, throat or genital area.
- Lung problems (pneumonitis). PEMFEXY can cause serious lung problems that can lead to death. Tell your healthcare provider right away if you get any new or worsening symptoms of shortness of breath, cough, or fever.
- Radiation recall. Radiation recall is a skin reaction that can happen in people who have received radiation treatment in the past and are treated with PEMFEXY. Tell your healthcare provider if you get swelling, blistering, or a rash that looks like a sunburn in an area that was previously treated with radiation.

The most common side effects of PEMFEXY when given alone are:

- tiredness

- nausea

- loss of appetite

The most common side effects of PEMFEXY when given with cisplatin are:

- vomiting
- swelling or sores in your mouth or sore throat
- constipation

- low white blood cell counts (neutropenia)
- low platelet counts (thrombocytopenia)
- low red blood cell counts (anemia)

The most common side effects of PEMFEXY when given with pembrolizumab and platinum chemotherapy are:

- tiredness and weakness
- constipation
- loss of appetite
- vomiting
- shortness of breath

- nausea
- diarrhea
- rash
- cough
- fever

PEMFEXY may cause fertility problems in males. This may affect your ability to father a child. It is not known if these
effects are reversible. Talk to your healthcare provider if this is a concern for you.

Your healthcare provider will do blood tests to check for side effects during treatment with PEMFEXY. Your healthcare
provider may change your dose of PEMFEXY, delay treatment, or stop treatment if you have certain side effects.

Tell your healthcare provider if you have any side effect that bothers you or that does not go away.

These are not all of the possible side effects of PEMFEXY. For more information, ask your healthcare provider or pharmacist.

Call your doctor for medical advice about side effects. You may report side effects to FDA at 1-800-FDA-1088.

General information about the safe and effective use of PEMFEXY.

Medicines are sometimes prescribed for purposes other than those listed in a Patient Information leaflet. You can
ask your pharmacist or healthcare provider for information about PEMFEXY that is written for health professionals.

What are the ingredients in PEMFEXY?

Active ingredient: pemetrexed

Inactive ingredients: propylene glycol, tromethamine, and water for injection. Additional tromethamine or hydrochloric
acid may be added for pH adjustment.

Marketed by: Eagle Pharmaceuticals, Inc. Woodcliff Lake, NJ 07677

For more information, go to www.eagleus.com or call 1-855-318-2170

This Patient Information has been approved by the U.S. Food and Drug Administration.

December 2022